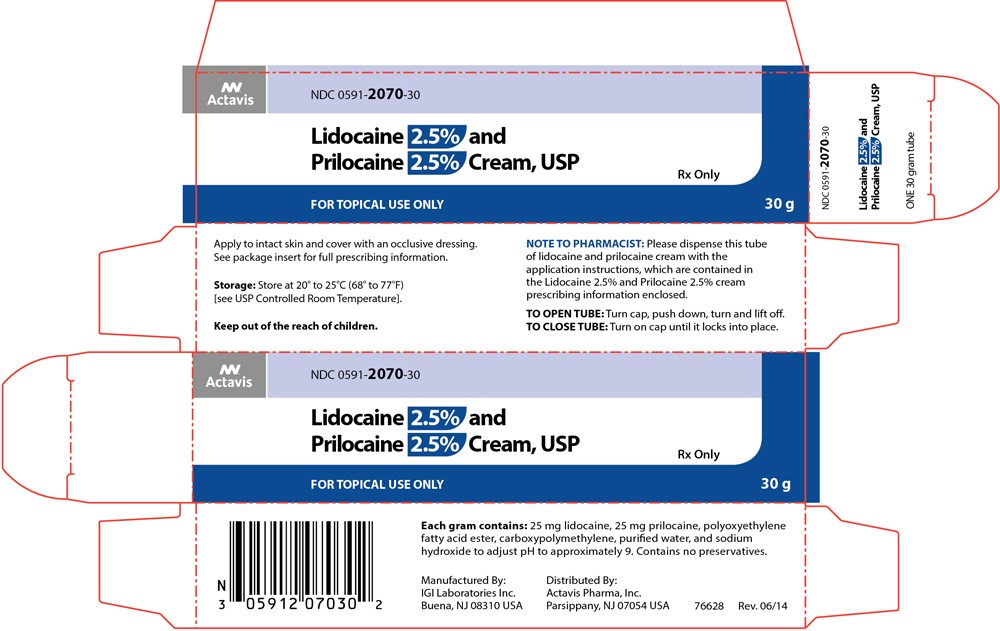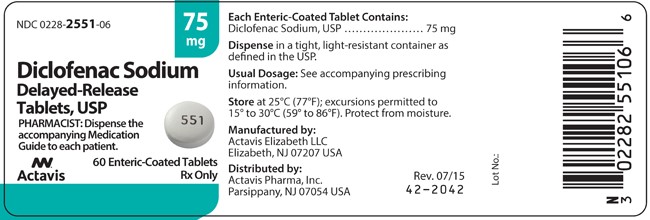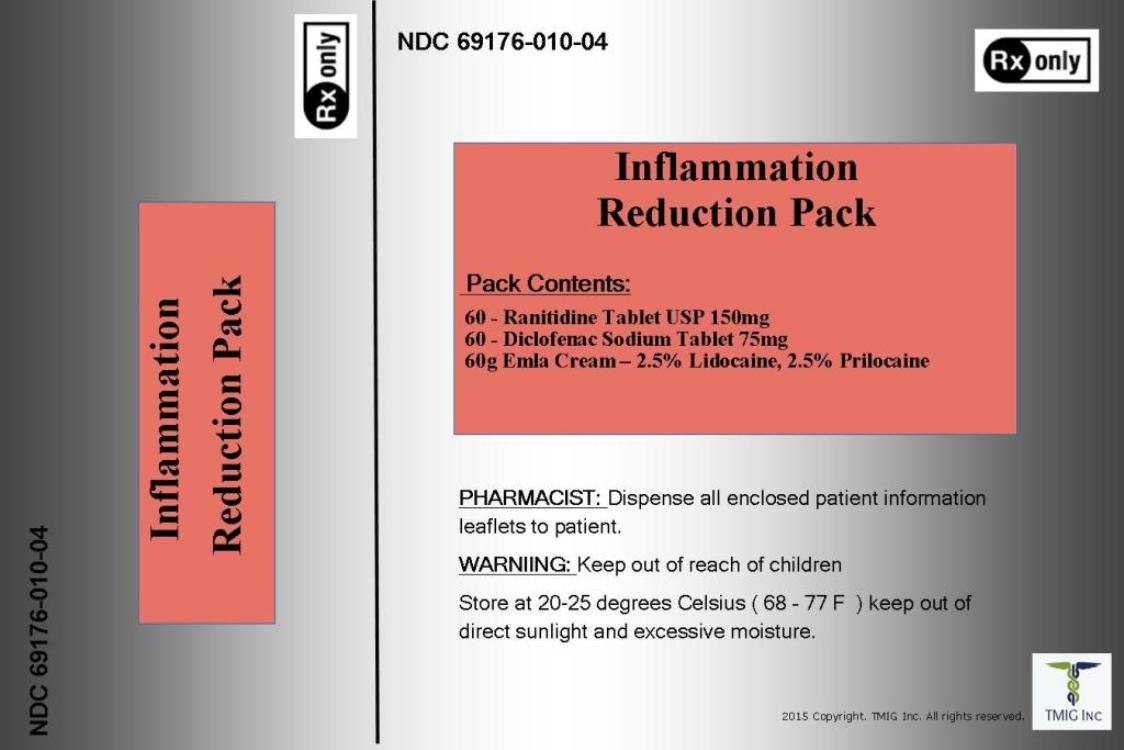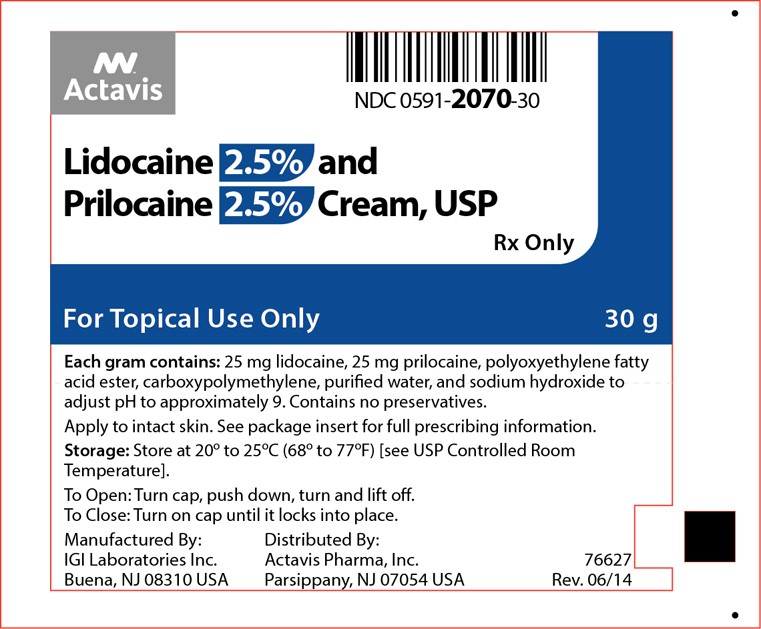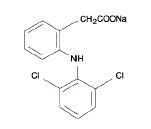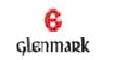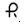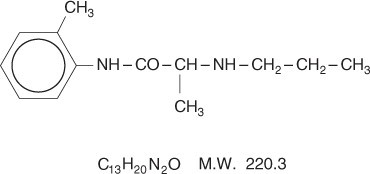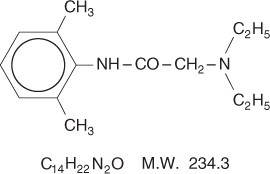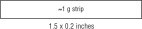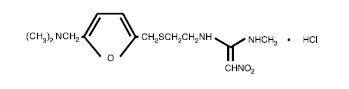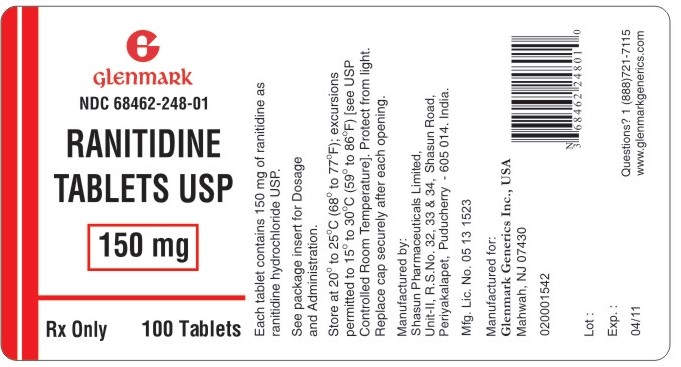 DRUG LABEL: Inflammation Reduction Pack
NDC: 69176-010 | Form: KIT | Route: TOPICAL
Manufacturer: TMIG, Inc.
Category: prescription | Type: HUMAN PRESCRIPTION DRUG LABEL
Date: 20151118

ACTIVE INGREDIENTS: LIDOCAINE 25 mg/1 g; PRILOCAINE 25 mg/1 g; DICLOFENAC SODIUM 75 mg/1 1; RANITIDINE HYDROCHLORIDE 150 mg/1 1
INACTIVE INGREDIENTS: PEG-55 HYDROGENATED CASTOR OIL; CARBOMER HOMOPOLYMER TYPE B (ALLYL SUCROSE CROSSLINKED); WATER; SODIUM HYDROXIDE; POLYSORBATE 80; SODIUM ALGINATE; STEARIC ACID; FERROSOFERRIC OXIDE; TITANIUM DIOXIDE; HYPROMELLOSES; LACTOSE MONOHYDRATE; MAGNESIUM STEARATE; POLYETHYLENE GLYCOLS; PROPYLENE GLYCOL; SILICON DIOXIDE; TALC; SODIUM STARCH GLYCOLATE TYPE A POTATO; CELLULOSE, MICROCRYSTALLINE; POLYVINYL ACETATE PHTHALATE; ALUMINUM HYDROXIDE; CROSCARMELLOSE SODIUM; SILICON DIOXIDE; FD&C RED NO. 40; TITANIUM DIOXIDE; TRIACETIN; HYPROMELLOSES; MAGNESIUM STEARATE; CELLULOSE, MICROCRYSTALLINE

Inflamation Reduction Pack
These highlights do not include all the information needed to use Inflammation Reduction Pack safely and effectively.see full prescribing information for Inflammation Reduction Pack
Inflammation Reduction Pack (Inflammation Reduction Pack) KIT for use.
Initial U.S. Approval:

Kit Description

Ranitidine Tablet USP 150mg

Diclofenac Sodium Tablet 75mg

Lidocaine 2.5% and Prilocaine 2.5% Cream, USP

Ranitidine hydrochloride

The active ingredient in ranitidine tablets USP 150 mg and 300 mg is ranitidine hydrochloride (HCl), USP, a histamine H2-receptor antagonist. Chemically it is N[2-[[[5-[(dimethylamino)methyl]-2-furanyl]methyl]thio]ethyl]-N'-methyl-2-nitro-1,1-ethenediamine, HCl. It has the following structure:
The empirical formula is C13H22N4O3S•HCl, representing a molecular weight of 350.87.
Ranitidine HCl USP is a white to pale yellow, granular substance that is soluble in water. It has a slightly bitter taste and sulfur like odor.
Each ranitidine tablet USP 150 mg for oral administration contains 168 mg of ranitidine HCl USP equivalent to 150 mg of ranitidine. Each tablet also contains the inactive ingredients microcrystalline cellulose, croscarmellose sodium, colloidal silicon dioxide, magnesium stearate, FD&C Red # 40 Aluminum Lake, hypromellose, titanium dioxide, triacetin.

Diclofenac sodium

Diclofenac sodium delayed-release tablets, USP are a benzeneacetic acid derivative. The chemical name is 2-[(2,6-dichlorophenyl)amino] benzeneacetic acid, monosodium salt. The molecular weight is 318.13. Its molecular formula is C14H10Cl2NNaO2, and it has the following structural formula
Each enteric-coated tablet for oral administration contains 50 mg or 75 mg of diclofenac sodium, USP. In addition, each tablet contains the following inactive ingredients: aluminum hydrate, colloidal silicon dioxide, hypromellose, lactose monohydrate, magnesium stearate, microcrystalline cellulose, polyethylene glycol, polysorbate 80, polyvinyl acetate phthalate, propylene glycol, silica, sodium alginate, sodium starch glycolate (Type A), stearic acid, synthetic black iron oxide, talc, and titanium dioxide.

Lidocaine 2.5% and Prilocaine 2.5% Cream, USP is an emulsion in which the oil phase is a eutectic mixture of lidocaine and prilocaine cream in a ratio of 1:1 by weight. This eutectic mixture has a melting point below room temperature and therefore both local anesthetics exist as a liquid oil rather than as crystals. It is packaged in 5 gram and 30 gram tubes.
Lidocaine is chemically designated as acetamide, 2-(diethylamino)-N-(2,6-dimethylphenyl), has an octanol: water partition ratio of 43 at pH 7.4, and has the following structure:
Prilocaine is chemically designated as propanamide, N-(2-methylphenyl)-2-(propylamino), has an octanol: water partition ratio of 25 at pH 7.4, and has the following structure:
Each gram of lidocaine and prilocaine cream contains lidocaine 25 mg, prilocaine 25 mg, polyoxyethylene fatty acid esters (as emulsifiers), carboxypolymethylene (as a thickening agent), sodium hydroxide to adjust to a pH approximating 9, and purified water to 1 gram. Lidocaine and prilocaine cream contains no preservative, however it passes the USP antimicrobial effectiveness test due to the pH. The specific gravity of lidocaine and prilocaine cream is 1.00.

RANITIDINE HYDROCHLORIDE

CLINICAL PHARMACOLOGY

Ranitidine is a competitive, reversible inhibitor of the action of histamine at the histamine H2-receptors, including receptors on the gastric cells. Ranitidine does not lower serum Ca++ in hypercalcemic states. Ranitidine is not an anticholinergic agent.

Pharmacokinetics:

Absorption:

Ranitidine is 50% absorbed after oral administration, compared to an intravenous (IV) injection with mean peak levels of 440 to 545 ng/mL occurring 2 to 3 hours after a 150-mg dose. Absorption is not significantly impaired by the administration of food or antacids. Propantheline slightly delays and increases peak blood levels of ranitidine, probably by delaying gastric emptying and transit time. In one study, simultaneous administration of high-potency antacid (150 mmol) in fasting subjects has been reported to decrease the absorption of ranitidine.

Distribution:

The volume of distribution is about 1.4 L/kg. Serum protein binding averages 15%.

Metabolism:

In humans, the N-oxide is the principal metabolite in the urine; however, this amounts to <4% of the dose. Other metabolites are the S-oxide (1%) and the desmethyl ranitidine (1%). The remainder of the administered dose is found in the stool. Studies in patients with hepatic dysfunction (compensated cirrhosis) indicate that there are minor, but clinically insignificant, alterations in ranitidine half-life, distribution, clearance, and bioavailability.

Excretion:

The principal route of excretion is the urine, with approximately 30% of the orally administered dose collected in the urine as unchanged drug in 24 hours. Renal clearance is about 410 mL/min, indicating active tubular excretion. The elimination half-life is 2.5 to 3 hours. Four patients with clinically significant renal function impairment (creatinine clearance 25 to 35 mL/min) administered 50 mg of ranitidine intravenously had an average plasma half-life of 4.8 hours, a ranitidine clearance of 29 mL/min, and a volume of distribution of 1.76 L/kg. In general, these parameters appear to be altered in proportion to creatinine clearance (see DOSAGE AND ADMINISTRATION).

Geriatrics:

The plasma half-life is prolonged and total clearance is reduced in the elderly population due to a decrease in renal function. The elimination half-life is 3 to 4 hours. Peak levels average 526 ng/mL following a 150-mg twice-daily dose and occur in about 3 hours (see PRECAUTIONS: Geriatric Use and DOSAGE AND ADMINISTRATION: Dosage Adjustment for Patients With Impaired Renal Function).

Pediatrics:

There are no significant differences in the pharmacokinetic parameter values for ranitidine in pediatric patients (from 1 month up to 16 years of age) and healthy adults when correction is made for body weight. The average bioavailability of ranitidine given orally to pediatric patients is 48% which is comparable to the bioavailability of ranitidine in the adult population. All other pharmacokinetic parameter values (t1/2, Vd, and CL) are similar to those observed with intravenous ranitidine use in pediatric patients. Estimates of Cmax and Tmax are displayed in Table 1.

Table 1. Ranitidine Pharmacokinetics in Pediatric Patients Following Oral Dosing
Population (age) | n | Dosage Form (dose) | Cmax (ng/mL) | Tmax (hours)
Gastric or duodenal ulcer (3.5 to 16 years) | 12 | Tablets (1 to 2 mg/kg) | 54 to 492 | 2.0

Plasma clearance measured in 2 neonatal patients (less than 1 month of age) was considerably lower (3 mL/min/kg) than children or adults and is likely due to reduced renal function observed in this population (see PRECAUTIONS: Pediatric Use and DOSAGE AND ADMINISTRATION: Pediatric Use).

Pharmacodynamics:

Serum concentrations necessary to inhibit 50% of stimulated gastric acid secretion are estimated to be 36 to 94 ng/mL. Following a single oral dose of 150 mg, serum concentrations of ranitidine are in this range up to 12 hours. However, blood levels bear no consistent relationship to dose or degree of acid inhibition.

Antisecretory Activity:

1. Effects on Acid Secretion:

Ranitidine inhibits both daytime and nocturnal basal gastric acid secretions as well as gastric acid secretion stimulated by food, betazole, and pentagastrin, as shown in Table 2.

Table 2. Effect of Oral Ranitidine on Gastric Acid Secretion
 | Time After Dose, hours | % Inhibition of Gastric Acid Output by Dose, mg
 | Time After Dose, hours | 75 - 80 | 100 | 150 | 200
Basal | Up to 4 |  | 99 | 95
Nocturnal | Up to 13 | 95 | 96 | 92
Betazole | Up to 3 |  | 97 | 99
Pentagastrin | Up to 5 | 58 | 72 | 72 | 80
Meal | Up to 3 |  | 73 | 79 | 95

It appears that basal-, nocturnal-, and betazole-stimulated secretions are most sensitive to inhibition by ranitidine, responding almost completely to doses of 100 mg or less, while pentagastrin- and food-stimulated secretions are more difficult to suppress.

2. Effects on Other Gastrointestinal Secretions:

Pepsin: Oral ranitidine does not affect pepsin secretion. Total pepsin output is reduced in proportion to the decrease in volume of gastric juice.

Intrinsic Factor: Oral ranitidine has no significant effect on pentagastrin-stimulated intrinsic factor secretion.

Serum Gastrin: Ranitidine has little or no effect on fasting or postprandial serum gastrin.

Other Pharmacologic Actions:

1. Gastric bacterial flora - increase in nitrate-reducing organisms, significance not known.
2. Prolactin levels - no effect in recommended oral or intravenous (IV) dosage, but small, transient, dose-related increases in serum prolactin have been reported after IV bolus injections of 100 mg or more.
3. Other pituitary hormones - no effect on serum gonadotropins, TSH, or GH. Possible impairment of vasopressin release.
4. No change in cortisol, aldosterone, androgen, or estrogen levels.
5. No antiandrogenic action.
6. No effect on count, motility, or morphology of sperm.

Pediatrics:

Oral doses of 6 to 10 mg/kg/day in 2 or 3 divided doses maintain gastric pH>4 throughout most of the dosing interval.

Clinical Trials

Active Duodenal Ulcer:

In a multicenter, double-blind, controlled, US study of endoscopically diagnosed duodenal ulcers; earlier healing was seen in the patients treated with ranitidine as shown in Table 3.

Table 3. Duodenal Ulcer Patient healing Rates
* All patients were permitted antacids as needed for relief of pain. †p < 0.0001.
 | Ranitidine * |  | Placebo*
 | Number Entered | Healed/Evaluable | Number Entered | Healed/Evaluable
Outpatients | 195 | 69/182 (38%) † | 188 | 31/164 (19%)
Week 2 | 195 | 69/182 (38%) † | 188 | 31/164 (19%)
Week 4 | 195 | 137/187 (73%) † | 188 | 76/168 (45%)

In these studies, patients treated with ranitidine reported a reduction in both daytime and nocturnal pain, and they also consumed less antacid than the placebo-treated patients.

Table 4. Mean Daily Doses of Antacid
 | Ulcer Healed | Ulcer Not Healed
Ranitidine | 0.06 | 0.71
Placebo | 0.71 | 1.43

Foreign studies have shown that patients heal equally well with 150 mg twice daily and 300 mg at bedtime (85% versus 84%, respectively) during a usual 4-week course of therapy. If patients require extended therapy of 8 weeks, the healing rate may be higher for 150 mg twice daily as compared to 300 mg at bedtime (92% versus 87%, respectively).

Studies have been limited to short-term treatment of acute duodenal ulcer. Patients whose ulcers healed during therapy had recurrences of ulcers at the usual rates.

Maintenance Therapy in Duodenal Ulcer:

Ranitidine has been found to be effective as maintenance therapy for patients following healing of acute duodenal ulcers. In 2 independent, double-blind, multicenter, controlled trials, the number of duodenal ulcers observed was significantly less in patients treated with ranitidine (150 mg at bedtime) than in patients treated with placebo over a 12-month period.

Table 5. Duodenal Ulcer Prevalence
% = Life table estimate.
RAN = ranitidine (ranitidine tablets USP)
PLC = placebo
*p < 0.05 (ranitidine tablets USP versus comparator)
Double-Blind, Multicenter, Placebo-Controlled Trials
Multicenter trial | Drug | Duodenal Ulcer Prevalence |  |  | No. of Patients
Multicenter trial | Drug | 0 - 4 Months | 0 - 8 Months | 0 - 12 Months | No. of Patients
USA | RAN | 20% * | 24% * | 35% * | 138
USA | PLC | 44% | 54% | 59% | 139
Foreign | RAN | 12% * | 21% * | 28% * | 174
Foreign | PLC | 56% | 64% | 68% | 165

As with other H2-antagonists, the factors responsible for the significant reduction in the prevalence of duodenal ulcers include prevention of recurrence of ulcers, more rapid healing of ulcers that may occur during maintenance therapy, or both.

Gastric Ulcer:

In a multicenter, double-blind, controlled, US study of endoscopically diagnosed gastric ulcers, earlier healing was seen in the patients treated with ranitidine as shown in Table 6.

Table 6. Gastric Ulcer Patient Healing Rates
* All patients were permitted antacids as needed for relief of pain. †p = 0.009.
 | Ranitidine * |  | Placebo*
 | Number Entered | Healed/Evaluable | Number Entered | Healed/Evaluable
Outpatients | 92 | 16/83 (19%) | 94 | 10/83 (12%)
Week 2 | 92 | 16/83 (19%) | 94 | 10/83 (12%)
Week 6 | 92 | 50/73 (68%) † | 94 | 35/69 (51%)

In this multicenter trial, significantly more patients treated with ranitidine became pain free during therapy.

Maintenance of Healing of Gastric Ulcers:

In 2 multicenter, double-blind, randomized, placebo-controlled, 12-month trials conducted in patients whose gastric ulcers had been previously healed, ranitidine 150 mg at bedtime was significantly more effective than placebo in maintaining healing of gastric ulcers.

Pathological Hypersecretory Conditions (such as Zollinger-Ellison syndrome):

Ranitidine inhibits gastric acid secretion and reduces occurrence of diarrhea, anorexia, and pain in patients with pathological hypersecretion associated with Zollinger-Ellison syndrome, systemic mastocytosis, and other pathological hypersecretory conditions (e.g., postoperative, "short-gut" syndrome, idiopathic). Use of ranitidine was followed by healing of ulcers in 8 of 19 (42%) patients who were intractable to previous therapy.

Gastroesophageal Reflux Disease (GERD):

In 2 multicenter, double-blind, placebo-controlled, 6-week trials performed in the United States and Europe, ranitidine 150 mg twice daily was more effective than placebo for the relief of heartburn and other symptoms associated with GERD. Ranitidine-treated patients consumed significantly less antacid than did placebo-treated patients.

The US trial indicated that ranitidine 150 mg twice daily significantly reduced the frequency of heartburn attacks and severity of heartburn pain within 1 to 2 weeks after starting therapy. The improvement was maintained throughout the 6-week trial period. Moreover, patient response rates demonstrated that the effect on heartburn extends through both the day and night time periods.

In 2 additional US multicenter, double-blind, placebo-controlled, 2-week trials, ranitidine 150 mg twice daily was shown to provide relief of heartburn pain within 24 hours of initiating therapy and a reduction in the frequency of severity of heartburn.

Erosive Esophagitis:

In 2 multicenter, double-blind, randomized, placebo-controlled, 12-week trials performed in the United States, ranitidine 150 mg 4 times daily was significantly more effective than placebo in healing endoscopically diagnosed erosive esophagitis and in relieving associated heartburn. The erosive esophagitis healing rates were as follows:

Table 7. Erosive Esophagitis Patient Healing Rates
* All patients were permitted antacids as needed for relief of pain. †p < 0.001 versus placebo.
 | Healed/Evaluable
 | Placebo * n=229 | Ranitidine 150 mg 4 times daily * n=215
Week 4 | 43/198 (22%) | 96/206 (47%) †
Week 8 | 63/176 (36%) | 142/200 (71%) †
Week 12 | 92/159 (58%) | 162/192 (84%) †

No additional benefit in healing of esophagitis or in relief of heartburn was seen with a ranitidine dose of 300 mg 4 times daily.

Maintenance of Healing of Erosive Esophagitis:

In 2 multicenter, double-blind, randomized, placebo-controlled, 48-week trials conducted in patients whose erosive esophagitis had been previously healed, ranitidine 150 mg twice daily was significantly more effective than placebo in maintaining healing of erosive esophagitis.

INDICATIONS AND USAGE

Ranitidine tablets USP are indicated in:

1. Short-term treatment of active duodenal ulcer. Most patients heal within 4 weeks. Studies available to date have not assessed the safety of ranitidine in uncomplicated duodenal ulcer for periods of more than 8 weeks.
2. Maintenance therapy for duodenal ulcer patients at reduced dosage after healing of acute ulcers. No placebo-controlled comparative studies have been carried out for periods of longer than 1 year.
3. The treatment of pathological hypersecretory conditions (e.g., Zollinger-Ellison syndrome and systemic mastocytosis).
4. Short-term treatment of active, benign gastric ulcer. Most patients heal within 6 weeks and the usefulness of further treatment has not been demonstrated. Studies available to date have not assessed the safety of ranitidine in uncomplicated, benign gastric ulcer for periods of more than 6 weeks.
5. Maintenance therapy for gastric ulcer patients at reduced dosage after healing of acute ulcers. Placebo-controlled studies have been carried out for 1 year.
6. Treatment of GERD. Symptomatic relief commonly occurs within 24 hours after starting therapy with ranitidine 150 mg twice daily.
7. Treatment of endoscopically diagnosed erosive esophagitis. Symptomatic relief of heartburn commonly occurs within 24 hours of therapy initiation with ranitidine 150 mg 4 times daily.
8. Maintenance of healing of erosive esophagitis. Placebo-controlled trials have been carried out for 48 weeks.

Concomitant antacids should be given as needed for pain relief to patients with active duodenal ulcer; active, benign gastric ulcer; hypersecretory states; GERD; and erosive esophagitis.

CONTRAINDICATIONS

Ranitidine tablets USP are contraindicated for patients known to have hypersensitivity to the drug or any of the ingredients (see PRECAUTIONS).

PRECAUTIONS

General:

1. Symptomatic response to therapy with ranitidine does not preclude the presence of gastric malignancy.
2. Since ranitidine is excreted primarily by the kidney, dosage should be adjusted in patients with impaired renal function (see DOSAGE AND ADMINISTRATION). Caution should be observed in patients with hepatic dysfunction since ranitidine is metabolized in the liver.
3. Rare reports suggest that ranitidine may precipitate acute porphyric attacks in patients with acute porphyria. Ranitidine should therefore be avoided in patients with a history of acute porphyria.

Laboratory Tests:

False-positive tests for urine protein with MULTISTIX® may occur during therapy with ranitidine, and therefore testing with sulfosalicylic acid is recommended.

Drug Interactions:

Ranitidine has been reported to affect the bioavailability of other drugs through several different mechanisms such as competition for renal tubular secretion, alteration of gastric pH, and inhibition of cytochrome P450 enzymes.

Procainamide: Ranitidine, a substrate of the renal organic cation transport system, may affect the clearance of other drugs eliminated by this route. High doses of ranitidine (e.g., such as those used in the treatment of Zollinger-Ellison syndrome) have been shown to reduce the renal excretion of procainamide and N-acetylprocainamide resulting in increased plasma levels of these drugs. Although this interaction is unlikely to be clinically relevant at usual ranitidine doses, it may be prudent to monitor for procainamide toxicity when administered with oral ranitidine at a dose exceeding 300 mg per day.

Warfarin: There have been reports of altered prothrombin time among patients on concomitant warfarin and ranitidine therapy. Due to the narrow therapeutic index, close monitoring of increased or decreased prothrombin time is recommended during concurrent treatment with ranitidine.

Ranitidine may alter the absorption of drugs in which gastric pH is an important determinant of bioavailability. This can result in either an increase in absorption (e.g., triazolam, midazolam, glipizide) or a decrease in absorption (e.g., ketoconazole, atazanavir, delavirdine, gefitinib). Appropriate clinical monitoring is recommended.

Atazanavir: Atazanavir absorption may be impaired based on known interactions with other agents that increase gastric pH. Use with caution. See atazanavir label for specific recommendations.

Delavirdine: Delavirdine absorption may be impaired based on known interactions with other agents that increase gastric pH. Chronic use of H2-receptor antagonists with delavirdine is not recommended.

Gefitinib : Gefitinib exposure was reduced by 44% with the coadministration of ranitidine and sodium bicarbonate (dosed to maintain gastric pH above 5.0). Use with caution.

Glipizide: In diabetic patients, glipizide exposure was increased by 34% following a single 150-mg dose of oral ranitidine. Use appropriate clinical monitoring when initiating or discontinuing ranitidine.

Ketoconazole: Oral ketoconazole exposure was reduced by up to 95% when oral ranitidine was coadministered in a regimen to maintain a gastric pH of 6 or above. The degree of interaction with usual dose of ranitidine (150 mg twice daily) is unknown.

Midazolam: Oral midazolam exposure in 5 healthy volunteers was increased by up to 65% when administered with oral ranitidine at a dose of 150 mg twice daily. However, in another interaction study in 8 volunteers receiving IV midazolam, a 300 mg oral dose of ranitidine increased midazolam exposure by about 9%. Monitor patients for excessive or prolonged sedation when ranitidine is coadministered with oral midazolam.

Triazolam: Triazolam exposure in healthy volunteers was increased by approximately 30% when administered with oral ranitidine at a dose of 150 mg twice daily. Monitor patients for excessive or prolonged sedation.

Carcinogenesis, Mutagenesis, Impairment of Fertility:

There was no indication of tumorigenic or carcinogenic effects in life-span studies in mice and rats at dosages up to 2,000 mg/kg per day.

Ranitidine was not mutagenic in standard bacterial tests (Salmonella, Escherichia coli) for mutagenicity at concentrations up to the maximum recommended for these assays.

In a dominant lethal assay, a single oral dose of 1,000 mg/kg to male rats was without effect on the outcome of 2 matings per week for the next 9 weeks.

Pregnancy:

Teratogenic Effects:

Pregnancy Category B. Reproduction studies have been performed in rats and rabbits at doses up to 160 times the human dose and have revealed no evidence of impaired fertility or harm to the fetus due to ranitidine. There are, however no adequate and well-controlled studies in pregnant women. Because animal reproduction studies are not always predictive of human response, this drug should be used during pregnancy only if clearly needed.

Nursing Mothers:

Ranitidine is secreted in human milk. Caution should be exercised when ranitidine is administered to a nursing mother.

Pediatric Use:

The safety and effectiveness of ranitidine have been established in the age-group of 1 month to 16 years for the treatment of duodenal and gastric ulcers, gastroesophageal reflux disease and erosive esophagitis, and the maintenance of healed duodenal and gastric ulcer. Use of ranitidine in this age-group is supported by adequate and well-controlled studies in adults, as well as additional pharmacokinetic data in pediatric patients and an analysis of the published literature (see CLINICAL PHARMACOLOGY: Pediatrics and DOSAGE AND ADMINISTRATION: Pediatric Use).

Safety and effectiveness in pediatric patients for the treatment of pathological hypersecretory conditions or the maintenance of healing of erosive esophagitis have not been established.

Safety and effectiveness in neonates (less than 1 month of age) have not been established (see CLINICAL PHARMACOLOGY: Pediatrics).

Geriatric Use:

Of the total number of subjects enrolled in US and foreign controlled clinical trials of oral formulations of ranitidine, for which there were subgroup analyses, 4,197 were 65 and over, while 899 were 75 and over. No overall differences in safety or effectiveness were observed between these subjects and younger subjects, and other reported clinical experience has not identified differences in responses between the elderly and younger patients, but greater sensitivity of some older individuals cannot be ruled out.

This drug is known to be substantially excreted by the kidney and the risk of toxic reactions to this drug may be greater in patients with impaired renal function. Because elderly patients are more likely to have decreased renal function, caution should be exercised in dose selection, and it may be useful to monitor renal function. (see CLINICAL PHARMACOLOGY: Pharmacokinetics: Geriatrics and DOSAGE AND ADMINISTRATION: Dosage Adjustment for Patients with Impaired Renal Function).

ADVERSE REACTIONS

The following have been reported as events in clinical trials or in the routine management of patients treated with ranitidine. The relationship to therapy with ranitidine has been unclear in many cases. Headache, sometimes severe, seems to be related to administration of ranitidine.

Central Nervous System:

Rarely, malaise, dizziness, somnolence, insomnia, and vertigo. Rare cases of reversible mental confusion, agitation, depression, and hallucinations have been reported, predominantly in severely ill elderly patients. Rare cases of reversible blurred vision suggestive of a change in accommodation have been reported. Rare reports of reversible involuntary motor disturbances have been received.

Cardiovascular:

As with other H2-blockers, rare reports of arrhythmias such as tachycardia, bradycardia, atrioventricular block, and premature ventricular beats.

Gastrointestinal:

Constipation, diarrhea, nausea/vomiting, abdominal discomfort/pain, and rare reports of pancreatitis.

Hepatic:

There have been occasional reports of hepatocellular, cholestatic, or mixed hepatitis, with or without jaundice. In such circumstances, ranitidine should be immediately discontinued. These events are usually reversible, but in rare circumstances death has occurred. Rare cases of hepatic failure have also been reported. In normal volunteers, SGPT values were increased to at least twice the pretreatment levels in 6 of 12 subjects receiving 100 mg intavenously 4 times daily for 7 days, and in 4 of 24 subjects receiving 50 mg intravenously 4 times daily for 5 days.

Musculoskeletal:

Rare reports of arthralgias and myalgias.

Hematologic:

Blood count changes (leukopenia, granulocytopenia, and thrombocytopenia) have occurred in a few patients. These were usually reversible. Rare cases of agranulocytosis, pancytopenia, sometimes with marrow hypoplasia, and aplastic anemia and exceedingly rare cases of acquired immune hemolytic anemia have been reported.

Endocrine:

Controlled studies in animals and man have shown no stimulation of any pituitary hormone by ranitidine and no antiandrogenic activity, and cimetidine-induced gynecomastia and impotence in hypersecretory patients have resolved when ranitidine has been substituted. However, occasional cases of impotence, and loss of libido have been reported in male patients receiving ranitidine, but the incidence did not differ from that in the general population. Rare cases of breast symptoms and conditions, including galactorrhea and gynecomastia, have been reported in both males and females.

Integumentary:

Rash, including rare cases of erythema multiforme. Rare cases of alopecia and vasculitis.

Respiratory:

A large epidemiological study suggested an increased risk of developing pneumonia in current users of histamine-2-receptor antagonists (H2RAs) compared to patients who had stopped H2RA treatment, with an observed adjusted relative risk of 1.63 (95% CI, 1.07 - 2.48). However, a causal relationship between use of H2RAs and pneumonia has not been established.

Other:

Rare cases of hypersensitivity reactions (e.g., bronchospasm, fever, rash, eosinophilia), anaphylaxis, angioneurotic edema, acute interstitial nephritis, and small increases in serum creatinine.

OVERDOSAGE

There has been limited experience with overdosage. Reported acute ingestions of up to 18 g orally have been associated with transient adverse effects similar to those encountered in normal clinical experience (see ADVERSE REACTIONS). In addition, abnormalities of gait and hypotension have been reported.

When overdosage occurs, the usual measures to remove unabsorbed material from the gastrointestinal tract, clinical monitoring, and supportive therapy should be employed.

Studies in dogs receiving dosages of ranitidine in excess of 225 mg/kg/day have shown muscular tremors, vomiting, and rapid respiration. Single oral doses of 1,000 mg/kg in mice and rats were not lethal. Intravenous LD50 values in mice and rats were 77 and 83 mg/kg, respectively.

DOSAGE AND ADMINISTRATION

Active Duodenal Ulcer:

The current recommended adult oral dosage of ranitidine tablets USP for duodenal ulcer is 150 mg twice daily. An alternative dosage of 300 mg once daily after the evening meal or at bedtime can be used for patients in whom dosing convenience is important. The advantages of one treatment regimen compared to the other in a particular patient population have yet to be demonstrated (see Clinical Trials: Active Duodenal Ulcer). Smaller doses have been shown to be equally effective in inhibiting gastric acid secretion in US studies, and several foreign trials have shown that 100 mg twice daily is as effective as the 150-mg dose.

Antacid should be given as needed for relief of pain (see CLINICAL PHARMACOLOGY: Pharmacokinetics).

Maintenance of Healing of Duodenal Ulcers:

The current recommended adult oral dosage is 150 mg at bedtime.

Pathological Hypersecretory Conditions (such as Zollinger-Ellison syndrome):

The current recommended adult oral dosage is 150 mg twice daily. In some patients it may be necessary to administer ranitidine 150-mg doses more frequently. Dosages should be adjusted to individual patient needs, and should continue as long as clinically indicated. Dosages up to 6 g/day have been employed in patients with severe disease.

Benign Gastric Ulcer:

The current recommended adult oral dosage is 150 mg twice daily.

Maintenance of Healing of Gastric Ulcers:

The current recommended adult oral dosage is 150 mg at bedtime.

GERD:

The current recommended adult oral dosage is 150 mg twice daily.

Erosive Esophagitis:

The current recommended adult oral dosage is 150 mg 4 times daily.

Maintenance of Healing of Erosive Esophagitis:

The current recommended adult oral dosage is 150 mg twice daily.

Pediatric Use:

The safety and effectiveness of ranitidine have been established in the age-group of 1 month to 16 years. There is insufficient information about the pharmacokinetics of ranitidine in neonatal patients (less than 1 month of age) to make dosing recommendations.

The following 3 subsections provide dosing information for each of the pediatric indications.

Treatment of Duodenal and Gastric Ulcers:

The recommended oral dose for the treatment of active duodenal and gastric ulcers is 2 to 4 mg/kg twice daily to a maximum of 300 mg/day. This recommendation is derived from adult clinical studies and pharmacokinetic data in pediatric patients.

Maintenance of Healing of Duodenal and Gastric Ulcers:

The recommended oral dose for the maintenance of healing of duodenal and gastric ulcers is 2 to 4 mg/kg once daily to a maximum of 150 mg/day. This recommendation is derived from adult clinical studies and pharmacokinetic data in pediatric patients.

Treatment of GERD and Erosive Esophagitis:

Although limited data exist for these conditions in pediatric patients, published literature supports a dosage of 5 to 10 mg/kg/day, usually given as 2 divided doses.

Dosage Adjustment for Patients With Impaired Renal Function:

On the basis of experience with a group of subjects with severely impaired renal function treated with ranitidine, the recommended dosage in patients with a creatinine clearance <50 mL/min is 150 mg every 24 hours. Should the patient's condition require, the frequency of dosing may be increased to every 12 hours or even further with caution. Hemodialysis reduces the level of circulating ranitidine. Ideally, the dosing schedule should be adjusted so that the timing of a scheduled dose coincides with the end of hemodialysis.

Elderly patients are more likely to have decreased renal function, therefore caution should be exercised in dose selection, and it may be useful to monitor renal function (see CLINICAL PHARMACOLGOY: Pharmacokinetics: Geriatrics and PRECAUTIONS: Geriatric Use).

HOW SUPPLIED

Ranitidine tablets USP 150 mg (ranitidine HCl USP equivalent to 150 mg of ranitidine) are pink colored, circular, biconvex, beveled edge film coated tablets with "G51" engraved on one side and "150" on the other side. They are available in bottles of 60 (NDC 68462-248-60), 100 (NDC 68462-248-01), and 500 (NDC 68462-248-05) tablets.

Store at 20° to 25°C (68° to 77°F); excursions permitted to 15 o to 30 o C (59 o to 86 o F) [see USP Controlled Room Temperature]. Protect from light. Replace cap securely after each opening.

Manufactured by:

Shasun Pharmaceuticals Limited,

Unit-II,
R.S. No. 32, 33 & 34, Shasun Road, Periyakalapet,
Puducherry - 605 014. India.

Manufactured for:

Glenmark Generics Inc., USA
Mahwah, NJ 07430

Questions? 1 (888)721-7115
www.glenmarkgenerics.com

April 2011

MULTISTIX is a registered trademark of Bayer Healthcare LLC.

DICLOFENAC SODIUM

CLINICAL PHARMACOLOGY

Pharmacodynamics

Diclofenac sodium delayed-release tablets, USP are a non-steroidal anti-inflammatory drug (NSAID) that exhibits anti-inflammatory, analgesic, and antipyretic activities in animal models. The mechanism of action of diclofenac sodium delayed-release, like that of other NSAIDs, is not completely understood but may be related to prostaglandin synthetase inhibition.

Pharmacokinetics

Absorption

Diclofenac is 100% absorbed after oral administration compared to IV administration as measured by urine recovery. However, due to first-pass metabolism, only about 50% of the absorbed dose is systemically available (see Table 1). Food has no significant effect on the extent of diclofenac absorption. However, there is usually a delay in the onset of absorption of 1 to 4.5 hours and a reduction in peak plasma levels of <20%.

Table 1. Pharmacokinetic Parameters for Diclofenac
 | Normal Healthy Adults
PK Parameter | (20 to 48 yrs.)
 |  | Coefficient of
 | Mean | Variation (%)
Absolute
Bioavailability (%)
[N = 7] | 55 | 40
Tmax (hr)
[N = 56] | 2.3 | 69
Oral Clearance (CL/F; mL/min)
[N = 56] | 582 | 23
Renal Clearance
(% unchanged drug in urine) | <1 | --
[N = 7]
Apparent Volume of
Distribution (V/F; L/kg)
[N = 56] | 1.4 | 58
Terminal Half-life (hr)
[N = 56] | 2.3 | 48

Distribution

The apparent volume of distribution (V/F) of diclofenac sodium is 1.4 L/kg.

Diclofenac is more than 99% bound to human serum proteins, primarily to albumin. Serum protein binding is constant over the concentration range (0.15 to 105 mcg/mL) achieved with recommended doses.

Diclofenac diffuses into and out of the synovial fluid. Diffusion into the joint occurs when plasma levels are higher than those in the synovial fluid, after which the process reverses and synovial fluid levels are higher than plasma levels. It is not known whether diffusion into the joint plays a role in the effectiveness of diclofenac.

Metabolism

Five diclofenac metabolites have been identified in human plasma and urine. The metabolites include 4'-hydroxy-, 5-hydroxy-, 3'-hydroxy-, 4',5-dihydroxy- and 3'-hydroxy-4'-methoxy diclofenac. The major diclofenac metabolite, 4'-hydroxy-diclofenac, has very weak pharmacologic activity. The formation of 4'-hydroxy- diclofenac is primarily mediated by CPY2C9. Both diclofenac and its oxidative metabolites undergo glucuronidation or sulfation followed by biliary excretion. Acylglucuronidation mediated by UGT2B7 and oxidation mediated by CPY2C8 may also play a role in diclofenac metabolism. CYP3A4 is responsible for the formation of minor metabolites, 5-hydroxy- and 3'-hydroxy-diclofenac. In patients with renal dysfunction, peak concentrations of metabolites 4'-hydroxy- and 5-hydroxy-diclofenac were approximately 50% and 4% of the parent compound after single oral dosing compared to 27% and 1% in normal healthy subjects.

Excretion

Diclofenac is eliminated through metabolism and subsequent urinary and biliary excretion of the glucuronide and the sulfate conjugates of the metabolites. Little or no free unchanged diclofenac is excreted in the urine. Approximately 65% of the dose is excreted in the urine and approximately 35% in the bile as conjugates of unchanged diclofenac plus metabolites. Because renal elimination is not a significant pathway of elimination for unchanged diclofenac, dosing adjustment in patients with mild to moderate renal dysfunction is not necessary. The terminal half-life of unchanged diclofenac is approximately 2 hours.

Drug Interactions

When co-administered with voriconazole (inhibitor of CYP2C9, 2C19 and 3A4 enzyme), the Cmax and AUC of diclofenac increased by 114% and 78%, respectively (see PRECAUTIONS, Drug Interactions).

Special Populations

Pediatric : The pharmacokinetics of diclofenac sodium delayed-release has not been investigated in pediatric patients.

Race : Pharmacokinetic differences due to race have not been identified.

Hepatic Insufficiency : Hepatic metabolism accounts for almost 100% of diclofenac sodium delayed-release elimination, so patients with hepatic disease may require reduced doses of diclofenac sodium delayed-release compared to patients with normal hepatic function.

Renal Insufficiency : Diclofenac pharmacokinetics has been investigated in subjects with renal insufficiency. No differences in the pharmacokinetics of diclofenac have been detected in studies of patients with renal impairment. In patients with renal impairment (inulin clearance 60 to 90, 30 to 60, and <30 mL/min; N=6 in each group), AUC values and elimination rate were comparable to those in healthy subjects.

INDICATIONS AND USAGE

Carefully consider the potential benefits and risks of diclofenac sodium delayed-release tablets, USP and other treatment options before deciding to use diclofenac sodium delayed-release tablets, USP. Use the lowest effective dose for the shortest duration consistent with individual patient treatment goals (see WARNINGS).

Diclofenac sodium delayed-release tablets are indicated:

- For relief of the signs and symptoms of osteoarthritis
- For relief of the signs and symptoms of rheumatoid arthritis
- For acute or long-term use in the relief of signs and symptoms of ankylosing spondylitis

CONTRAINDICATIONS

Diclofenac sodium delayed-release tablets, USP are contraindicated in patients with known hypersensitivity to diclofenac.

Diclofenac sodium delayed-release should not be given to patients who have experienced asthma, urticaria, or other allergic-type reactions after taking aspirin or other NSAIDs. Severe, rarely fatal, anaphylactic-like reactions to NSAIDs have been reported in such patients (see WARNINGS, Anaphylactoid Reactions , and PRECAUTIONS, Preexisting Asthma).

Diclofenac sodium delayed-release is contraindicated in the setting of coronary artery bypass graft (CABG) surgery (see WARNINGS).

WARNINGS

Cardiovascular Effects

Cardiovascular Thrombotic Events

Clinical trials of several COX-2 selective and nonselective NSAIDs of up to three years duration have shown an increased risk of serious cardiovascular (CV) thrombotic events, including myocardial infarction (MI) and stroke, which can be fatal. Based on available data, it is unclear that the risk for CV thrombotic events is similar for all NSAIDs. The relative increase in serious CV thrombotic events over baseline conferred by NSAID use appears to be similar in those with and without known CV disease or risk factors for CV disease. However, patients with known CV disease or risk factors had a higher absolute incidence of excess serious CV thrombotic events, due to their increased baseline rate. Some observational studies found that this increased risk of serious CV thrombotic events began as early as the first weeks of treatment. The increase in CV thrombotic risk has been observed most consistently at higher doses.

To minimize the potential risk for an adverse CV event in NSAID-treated patients, use the lowest effective dose for the shortest duration possible. Physicians and patients should remain alert for the development of such events, throughout the entire treatment course, even in the absence of previous CV symptoms. Patients should be informed about the symptoms of serious CV events and the steps to take if they occur.

There is no consistent evidence that concurrent use of aspirin mitigates the increased risk of serious CV thrombotic events associated with NSAID use. The concurrent use of aspirin and an NSAID, such as diclofenac, increases the risk of serious gastrointestinal (GI) events (see WARNINGS).

Status Post Coronary Artery Bypass Graft (CABG) Surgery

Two large, controlled clinical trials of a COX-2 selective NSAID for the treatment of pain in the first 10 to 14 days following CABG surgery found an increased incidence of myocardial infarction and stroke. NSAIDs are contraindicated in the setting of CABG (see CONTRAINDICATIONS).

Post-MI Patients

Observational studies conducted in the Danish National Registry have demonstrated that patients treated with NSAIDs in the post-MI period were at increased risk of reinfarction, CV-related death, and all-cause mortality beginning in the first week of treatment. In this same cohort, the incidence of death in the first year post MI was 20 per 100 person years in NSAID-treated patients compared to 12 per 100 person years in non-NSAID exposed patients. Although the absolute rate of death declined somewhat after the first year post-MI, the increased relative risk of death in NSAID users persisted over at least the next four years of follow-up.

Avoid the use of diclofenac sodium delayed-release in patients with a recent MI unless the benefits are expected to outweigh the risk of recurrent CV thrombotic events. If diclofenac sodium delayed-release is used in patients with a recent MI, monitor patients for signs of cardiac ischemia.

Hypertension

NSAIDs can lead to onset of new hypertension or worsening of preexisting hypertension, either of which may contribute to the increased incidence of CV events. Patients taking thiazides or loop diuretics may have impaired response to these therapies when taking NSAIDs. NSAIDs, including diclofenac sodium delayed-release should be used with caution in patients with hypertension. Blood pressure (BP) should be monitored closely during the initiation of NSAID treatment and throughout the course of therapy.

Heart Failure and Edema

The Coxib and traditional NSAID Trialists' Collaboration meta-analysis of randomized controlled trials demonstrated an approximately two-fold increase in hospitalizations for heart failure in COX-2 selective-treated patients and nonselective NSAID-treated patients compared to placebo-treated patients. In a Danish National Registry study of patients with heart failure, NSAID use increased the risk of MI, hospitalization for heart failure, and death.

Additionally, fluid retention and edema have been observed in some patients treated with NSAIDs. Use of diclofenac may blunt the CV effects of several therapeutic agents used to treat these medical conditions [e.g., diuretics, ACE inhibitors, or angiotensin receptor blockers (ARBs)] (see Drug Interactions).

Avoid the use of diclofenac sodium delayed-release in patients with severe heart failure unless the benefits are expected to outweigh the risk of worsening heart failure. If diclofenac sodium delayed-release is used in patients with severe heart failure, monitor patients for signs of worsening heart failure.

Gastrointestinal (GI) Effects - Risk of GI Ulceration, Bleeding, and Perforation

NSAIDs, including diclofenac sodium delayed-release, can cause serious gastrointestinal (GI) adverse events including inflammation, bleeding, ulceration, and perforation of the stomach, small intestine, or large intestine, which can be fatal. These serious adverse events can occur at any time, with or without warning symptoms, in patients treated with NSAIDs. Only one in five patients, who develop a serious upper GI adverse event on NSAID therapy, is symptomatic. Upper GI ulcers, gross bleeding, or perforation caused by NSAIDs occur in approximately 1% of patients treated for 3 to 6 months, and in about 2% to 4% of patients treated for one year. These trends continue with longer duration of use, increasing the likelihood of developing a serious GI event at some time during the course of therapy. However, even short-term therapy is not without risk.

NSAIDs should be prescribed with extreme caution in those with a prior history of ulcer disease or gastrointestinal bleeding. Patients with a prior history of peptic ulcer disease and/or gastrointestinal bleeding who use NSAIDs have a greater than 10-fold increased risk for developing a GI bleed compared to patients with neither of these risk factors. Other factors that increase the risk for GI bleeding in patients treated with NSAIDs include concomitant use of oral corticosteroids or anticoagulants, longer duration of NSAID therapy, smoking, use of alcohol, older age, and poor general health status. Most spontaneous reports of fatal GI events are in elderly or debilitated patients and therefore, special care should be taken in treating this population.

To minimize the potential risk for an adverse GI event in patients treated with an NSAID, the lowest effective dose should be used for the shortest possible duration. Patients and physicians should remain alert for signs and symptoms of GI ulceration and bleeding during NSAID therapy and promptly initiate additional evaluation and treatment if a serious GI adverse event is suspected. This should include discontinuation of the NSAID until a serious GI adverse event is ruled out. For high risk patients, alternate therapies that do not involve NSAIDs should be considered.

Renal Effects

Caution should be used when initiating treatment with diclofenac sodium delayed-release in patients with considerable dehydration.

Long-term administration of NSAIDs has resulted in renal papillary necrosis and other renal injury. Renal toxicity has also been seen in patients in whom renal prostaglandins have a compensatory role in the maintenance of renal perfusion. In these patients, administration of a nonsteroidal anti-inflammatory drug may cause a dose-dependent reduction in prostaglandin formation and, secondarily, in renal blood flow, which may precipitate overt renal decompensation. Patients at greatest risk of this reaction are those with impaired renal function, heart failure, liver dysfunction, those taking diuretics and ACE inhibitors, and the elderly. Discontinuation of NSAID therapy is usually followed by recovery to the pretreatment state.

Advanced Renal Disease

No information is available from controlled clinical studies regarding the use of diclofenac sodium delayed-release in patients with advanced renal disease. Therefore, treatment with diclofenac sodium delayed-release is not recommended in these patients with advanced renal disease. If diclofenac sodium delayed-release therapy must be initiated, close monitoring of the patient's renal function is advisable.

Hepatic Effects

Elevations of one or more liver tests may occur during therapy with diclofenac sodium delayed-release. These laboratory abnormalities may progress, may remain unchanged, or may be transient with continued therapy. Borderline elevations (i.e., less than 3 times the ULN [ULN = the upper limit of the normal range]) or greater elevations of transaminases occurred in about 15% of diclofenac-treated patients. Of the markers of hepatic function, ALT (SGPT) is recommended for the monitoring of liver injury.

In clinical trials, meaningful elevations (i.e., more than 3 times the ULN) of AST (GOT) (ALT was not measured in all studies) occurred in about 2% of approximately 5,700 patients at some time during diclofenac treatment. In a large, open-label, controlled trial of 3,700 patients treated for 2 to 6 months, patients were monitored first at 8 weeks and 1,200 patients were monitored again at 24 weeks. Meaningful elevations of ALT and/or AST occurred in about 4% of patients and included marked elevations (i.e., more than 8 times the ULN) in about 1% of the 3,700 patients. In that open-label study, a higher incidence of borderline (less than 3 times the ULN), moderate (3 to 8 times the ULN), and marked (>8 times the ULN) elevations of ALT or AST was observed in patients receiving diclofenac when compared to other NSAIDs. Elevations in transaminases were seen more frequently in patients with osteoarthritis than in those with rheumatoid arthritis.

Almost all meaningful elevations in transaminases were detected before patients became symptomatic. Abnormal tests occurred during the first 2 months of therapy with diclofenac in 42 of the 51 patients in all trials who developed marked transaminase elevations.

In postmarketing reports, cases of drug-induced hepatotoxicity have been reported in the first month, and in some cases, the first 2 months of therapy, but can occur at any time during treatment with diclofenac. Postmarketing surveillance has reported cases of severe hepatic reactions, including liver necrosis, jaundice, fulminant hepatitis with and without jaundice, and liver failure. Some of these reported cases resulted in fatalities or liver transplantation.

Physicians should measure transaminases periodically in patients receiving long-term therapy with diclofenac, because severe hepatotoxicity may develop without a prodrome of distinguishing symptoms. The optimum times for making the first and subsequent transaminase measurements are not known. Based on clinical trial data and postmarketing experiences, transaminases should be monitored within 4 to 8 weeks after initiating treatment with diclofenac. However, severe hepatic reactions can occur at any time during treatment with diclofenac.

If abnormal liver tests persist or worsen, if clinical signs and/or symptoms consistent with liver disease develop, or if systemic manifestations occur (e.g., eosinophilia, rash, abdominal pain, diarrhea, dark urine, etc.), diclofenac sodium delayed-release should be discontinued immediately.

To minimize the possibility that hepatic injury will become severe between transaminase measurements, physicians should inform patients of the warning signs and symptoms of hepatotoxicity (e.g., nausea, fatigue, lethargy, diarrhea, pruritus, jaundice, right upper quadrant tenderness, and "flu-like" symptoms), and the appropriate action patients should take if these signs and symptoms appear.

To minimize the potential risk for an adverse liver related event in patients treated with diclofenac sodium delayed-release, the lowest effective dose should be used for the shortest duration possible. Caution should be exercised in prescribing diclofenac sodium delayed-release with concomitant drugs that are known to be potentially hepatotoxic (e.g., antibiotics, anti-epileptics).

Anaphylactic Reactions

As with other NSAIDs, anaphylactic reactions may occur both in patients with the aspirin triad and in patients without known sensitivity to NSAIDs or known prior exposure to diclofenac sodium delayed-release. Diclofenac sodium delayed-release should not be given to patients with the aspirin triad. This symptom complex typically occurs in asthmatic patients who experience rhinitis with or without nasal polyps, or who exhibit severe, potentially fatal bronchospasm after taking aspirin or other NSAIDs. (See CONTRAINDICATIONS and PRECAUTIONS, Preexisting Asthma .) Anaphylaxis-type reactions have been reported with NSAID products, including with diclofenac products, such as diclofenac sodium delayed-release. Emergency help should be sought in cases where an anaphylactic reaction occurs.

Skin Reactions

NSAIDs, including diclofenac sodium delayed-release, can cause serious skin adverse events such as exfoliative dermatitis, Stevens-Johnson Syndrome (SJS), and toxic epidermal necrolysis (TEN), which can be fatal. These serious events may occur without warning. Patients should be informed about the signs and symptoms of serious skin manifestations and use of the drug should be discontinued at the first appearance of skin rash or any other sign of hypersensitivity.

Pregnancy

In late pregnancy, as with other NSAIDs, diclofenac sodium delayed-release should be avoided because it may cause premature closure of the ductus arteriosus.

PRECAUTIONS

General

Diclofenac sodium delayed-release tablets, USP cannot be expected to substitute for corticosteroids or to treat corticosteroid insufficiency. Abrupt discontinuation of corticosteroids may lead to disease exacerbation. Patients on prolonged corticosteroid therapy should have their therapy tapered slowly if a decision is made to discontinue corticosteroids.

The pharmacological activity of diclofenac sodium delayed-release in reducing fever and inflammation may diminish the utility of these diagnostic signs in detecting complications of presumed noninfectious, painful conditions.

Hematological Effects

Anemia is sometimes seen in patients receiving NSAIDs, including diclofenac sodium delayed-release. This may be due to fluid retention, occult or gross GI blood loss, or an incompletely described effect upon erythropoiesis. Patients on long-term treatment with NSAIDs, including diclofenac sodium delayed-release, should have their hemoglobin or hematocrit checked if they exhibit any signs or symptoms of anemia.

NSAIDs inhibit platelet aggregation and have been shown to prolong bleeding time in some patients. Unlike aspirin, their effect on platelet function is quantitatively less, of shorter duration, and reversible. Patients receiving diclofenac sodium delayed-release who may be adversely affected by alterations in platelet function, such as those with coagulation disorders or patients receiving anticoagulants, should be carefully monitored.

Preexisting Asthma

Patients with asthma may have aspirin-sensitive asthma. The use of aspirin in patients with aspirin-sensitive asthma has been associated with severe bronchospasm which can be fatal. Since cross-reactivity, including bronchospasm, between aspirin and other nonsteroidal anti-inflammatory drugs has been reported in such aspirin-sensitive patients, diclofenac sodium delayed-release should not be administered to patients with this form of aspirin sensitivity and should be used with caution in patients with preexisting asthma.

Information for Patients

Patients should be informed of the following information before initiating therapy with an NSAID and periodically during the course of ongoing therapy. Patients should also be encouraged to read the NSAID Medication Guide that accompanies each prescription dispensed.

1. Cardiovascular Thrombotic Events Advise patients to be alert for the symptoms of cardiovascular thrombotic events, including chest pain, shortness of breath, weakness, or slurring of speech, and to report any of these symptoms to their health care provider immediately (see WARNINGS).
2. Diclofenac sodium delayed-release, like other NSAIDs, can cause GI discomfort and, rarely, more serious GI side effects, such as ulcers and bleeding, which may result in hospitalization and even death. Although serious GI tract ulcerations and bleeding can occur without warning symptoms, patients should be alert for the signs and symptoms of ulcerations and bleeding, and should ask for medical advice when observing any indicative sign or symptoms including epigastric pain, dyspepsia, melena, and hematemesis. Patients should be apprised of the importance of this follow-up (see WARNINGS, Gastrointestinal (GI) Effects: Risk of GI Ulceration, Bleeding, and Perforation).
3. Diclofenac sodium delayed-release, like other NSAIDs, can cause serious skin side effects such as exfoliative dermatitis, SJS, and TEN, which may result in hospitalizations and even death. Although serious skin reactions may occur without warning, patients should be alert for the signs and symptoms of skin rash and blisters, fever, or other signs of hypersensitivity such as itching, and should ask for medical advice when observing any indicative signs or symptoms. Patients should be advised to stop the drug immediately if they develop any type of rash and contact their physicians as soon as possible.
4. Heart Failure and Edema Advise patients to be alert for the symptoms of congestive heart failure including shortness of breath, unexplained weight gain, or edema and to contact their healthcare provider if such symptoms occur (see WARNINGS).
5. Patients should be informed of the warning signs and symptoms of hepatotoxicity (e.g., nausea, fatigue, lethargy, pruritus, jaundice, right upper quadrant tenderness, and "flu-like" symptoms). If these occur, patients should be instructed to stop therapy and seek immediate medical therapy. (see WARNINGS, Hepatic Effects).
6. Patients should be informed of the signs of an anaphylactic reaction (e.g., difficulty breathing, swelling of the face or throat). If these occur, patients should be instructed to seek immediate emergency help (see WARNINGS, Anaphylactic Reactions).
7. In late pregnancy, as with other NSAIDs, diclofenac sodium delayed-release should be avoided because it will cause premature closure of the ductus arteriosus.

Laboratory Tests

Because serious GI tract ulcerations and bleeding can occur without warning symptoms, physicians should monitor for signs or symptoms of GI bleeding. In patients on long-term treatment with NSAIDs, including diclofenac sodium delayed-release, the CBC and a chemistry profile (including transaminase levels) should be checked periodically. If clinical signs and symptoms consistent with liver or renal disease develop, systemic manifestations occur (e.g., eosinophilia, rash, etc.) or if abnormal liver tests persist or worsen, diclofenac sodium delayed-release should be discontinued.

Drug Interactions

Aspirin : When diclofenac sodium delayed-release is administered with aspirin, its protein binding is reduced. The clinical significance of this interaction is not known; however, as with other NSAIDs, concomitant administration of diclofenac and aspirin is not generally recommended because of the potential of increased adverse effects.

Methotrexate: NSAIDs have been reported to competitively inhibit methotrexate accumulation in rabbit kidney slices. This may indicate that they could enhance the toxicity of methotrexate. Caution should be used when NSAIDs are administered concomitantly with methotrexate.

Cyclosporine: Diclofenac sodium delayed-release, like other NSAIDs, may affect renal prostaglandins and increase the toxicity of certain drugs. Therefore, concomitant therapy with diclofenac sodium delayed-release may increase cyclosporine's nephrotoxicity. Caution should be used when diclofenac is administered concomitantly with cyclosporine.

ACE-Inhibitors : Reports suggest that NSAIDs may diminish the antihypertensive effect of ACE inhibitors. This interaction should be given consideration in patients taking NSAIDs concomitantly with ACE inhibitors.

Furosemide : Clinical studies, as well as postmarketing observations, have shown that diclofenac sodium delayed-release can reduce the natriuretic effect of furosemide and thiazides in some patients. This response has been attributed to inhibition of renal prostaglandin synthesis. During concomitant therapy with NSAIDs, the patient should be observed closely for signs of renal failure (see WARNINGS, Renal Effects), as well as to assure diuretic efficacy.

Lithium : NSAIDs have produced an elevation of plasma lithium levels and a reduction in renal lithium clearance. The mean minimum lithium concentration increased 15% and the renal clearance was decreased by approximately 20%. These effects have been attributed to inhibition of renal prostaglandin synthesis by the NSAID. Thus, when NSAIDs and lithium are administered concurrently, subjects should be observed carefully for signs of lithium toxicity.

Warfarin : The effects of warfarin and NSAIDs on GI bleeding are synergistic, such that users of both drugs together have a risk of serious GI bleeding higher than users of either drug alone.

CYP2C9 Inhibitors or Inducers : Diclofenac is metabolized by cytochrome P450 enzymes, predominantly by CYP2C9. Co-administration of diclofenac with CYP2C9 inhibitors (e.g. voriconazole) may enhance the exposure and toxicity of diclofenac whereas co-administration with CYP2C9 inducers (e.g. rifampin) may lead to compromised efficacy of diclofenac. Use caution when dosing diclofenac with CYP2C9 inhibitors or inducers; a dosage adjustment may be warranted (see CLINICAL PHARMACOLOGY, Pharmacokinetics, Drug Interactions).

Pregnancy

Teratogenic Effects: Pregnancy Category C

Reproductive studies conducted in rats and rabbits have not demonstrated evidence of developmental abnormalities. However, animal reproduction studies are not always predictive of human response. There are no adequate and well-controlled studies in pregnant women.

Nonteratogenic Effects : Because of the known effects of nonsteroidal anti-inflammatory drugs on the fetal cardiovascular system (closure of ductus arteriosus), use during pregnancy (particularly late pregnancy) should be avoided.

Labor and Delivery

In rat studies with NSAIDs, as with other drugs known to inhibit prostaglandin synthesis, an increased incidence of dystocia, delayed parturition, and decreased pup survival occurred. The effects of diclofenac sodium delayed-release on labor and delivery in pregnant women are unknown.

Nursing Mothers

It is not known whether this drug is excreted in human milk. Because many drugs are excreted in human milk and because of the potential for serious adverse reactions in nursing infants from diclofenac sodium delayed-release, a decision should be made whether to discontinue nursing or to discontinue the drug, taking into account the importance of the drug to the mother.

Pediatric Use

Safety and effectiveness in pediatric patients have not been established.

Geriatric Use

As with any NSAIDs, caution should be exercised in treating the elderly (65 years and older).

ADVERSE REACTIONS

In patients taking diclofenac sodium delayed-release tablets, USP or other NSAIDs, the most frequently reported adverse experiences occurring in approximately 1% to 10% of patients are:

Gastrointestinal experiences including: abdominal pain, constipation, diarrhea, dyspepsia, flatulence, gross bleeding/perforation, heartburn, nausea, GI ulcers (gastric/duodenal) and vomiting.

Abnormal renal function, anemia, dizziness, edema, elevated liver enzymes, headaches, increased bleeding time, pruritus, rashes and tinnitus.

Additional adverse experiences reported occasionally include:

Body as a Whole: fever, infection, sepsis

Cardiovascular System : congestive heart failure, hypertension, tachycardia, syncope

Digestive System: dry mouth, esophagitis, gastric/peptic ulcers, gastritis, gastrointestinal bleeding, glossitis, hematemesis, hepatitis, jaundice

Hemic and Lymphatic System : ecchymosis, eosinophilia, leukopenia, melena, purpura, rectal bleeding, stomatitis, thrombocytopenia

Metabolic and Nutritional: weight changes

Nervous System: anxiety, asthenia, confusion, depression, dream abnormalities, drowsiness, insomnia, malaise, nervousness, paresthesia, somnolence, tremors, vertigo

Respiratory System: asthma, dyspnea

Skin and Appendages : alopecia, photosensitivity, sweating increased

Special Senses: blurred vision

Urogenital System: cystitis, dysuria, hematuria, interstitial nephritis, oliguria/polyuria, proteinuria, renal failure

Other adverse reactions, which occur rarely are:

Body as a Whole: anaphylactic reactions, appetite changes, death

Cardiovascular System: arrhythmia, hypotension, myocardial infarction, palpitations, vasculitis

Digestive System: colitis, eructation, fulminant hepatitis with and without jaundice, liver failure, liver necrosis, pancreatitis

Hemic and Lymphatic System: agranulocytosis, hemolytic anemia, aplastic anemia, lymphadenopathy, pancytopenia

Metabolic and Nutritional: hyperglycemia

Nervous System: convulsions, coma, hallucinations, meningitis

Respiratory System: respiratory depression, pneumonia

Skin and Appendages: angioedema, toxic epidermal necrolysis, erythema multiforme, exfoliative dermatitis, Stevens-Johnson syndrome, urticaria

Special Senses: conjunctivitis, hearing impairment

To report SUSPECTED ADVERSE EVENTS, contact Actavis at 1-800-432-8534 or FDA at 1-800-FDA-1088 or http://www.fda.gov/ for voluntary reporting of adverse reactions.

OVERDOSAGE

Symptoms following acute NSAID overdoses are usually limited to lethargy, drowsiness, nausea, vomiting, and epigastric pain, which are generally reversible with supportive care. Gastrointestinal bleeding can occur. Hypertension, acute renal failure, respiratory depression and coma may occur, but are rare. Anaphylactoid reactions have been reported with therapeutic ingestion of NSAIDs, and may occur following an overdose.

Patients should be managed by symptomatic and supportive care following a NSAID overdose. There are no specific antidotes. Emesis and/or activated charcoal (60 to 100 g in adults, 1 to 2 g/kg in children) and/or osmotic cathartic may be indicated in patients seen within 4 hours of ingestion with symptoms or following a large overdose (5 to 10 times the usual dose). Forced diuresis, alkalinization of urine, hemodialysis, or hemoperfusion may not be useful due to high protein binding.

DOSAGE AND ADMINISTRATION

Carefully consider the potential benefits and risks of diclofenac sodium delayed-release tablets, USP and other treatment options before deciding to use diclofenac sodium delayed-release. Use the lowest effective dose for the shortest duration consistent with individual patient treatment goals (see WARNINGS).

After observing the response to initial therapy with diclofenac sodium delayed-release, the dose and frequency should be adjusted to suit an individual patient's needs.

For the relief of osteoarthritis, the recommended dosage is 100 to 150 mg/day in divided doses (50 mg b.i.d. or t.i.d., or 75 mg b.i.d.).

For the relief of rheumatoid arthritis, the recommended dosage is 150 to 200 mg/day in divided doses (50 mg t.i.d. or q.i.d., or 75 mg b.i.d.).

For the relief of ankylosing spondylitis, the recommended dosage is 100 to 125 mg/day, administered as 25 mg q.i.d., with an extra 25 mg dose at bedtime if necessary.

Different formulations of diclofenac (diclofenac sodium delayed-release tablets; diclofenac sodium extended-release tablets, USP; diclofenac potassium immediate-release tablets) are not necessarily bioequivalent even if the milligram strength is the same.

HOW SUPPLIED

Diclofenac Sodium Delayed-Release Tablets, USP are available as follows:

75 mg — Each white, round, enteric-coated tablet printed with
on one side and 551 on the other side with black ink contains 75 mg of Diclofenac Sodium, USP. Tablets are supplied in bottles of 60 (NDC 0228-2551-06), 100 (NDC 0228-2551-11), and 1000 (NDC 0228-2551-96).

Store at 25ºC (77ºF); excursions permitted to 15º to 30ºC (59ºto 86ºF).

Protect from moisture.

Dispense in a tight, light-resistant container as defined in the USP.

Manufactured by:
Actavis Elizabeth LLC
Elizabeth, NJ 07207 USA

Distributed by:
Actavis Pharma, Inc.
Parsippany, NJ 07054 USA

40-9184

Revised — August 2015

LIDOCAINE 2.5% AND PRILOCAINE 2.5%

CLINICAL PHARMACOLOGY

Mechanism of Action: Lidocaine and prilocaine cream applied to intact skin under occlusive dressing, provides dermal analgesia by the release of lidocaine and prilocaine from the cream into the epidermal and dermal layers of the skin and by the accumulation of lidocaine and prilocaine in the vicinity of dermal pain receptors and nerve endings. Lidocaine and prilocaine are amide-type local anesthetic agents. Both lidocaine and prilocaine stabilize neuronal membranes by inhibiting the ionic fluxes required for the initiation and conduction of impulses, thereby effecting local anesthetic action.

The onset, depth and duration of dermal analgesia on intact skin provided by lidocaine and prilocaine cream depend primarily on the duration of application. To provide sufficient analgesia for clinical procedures such as intravenous catheter placement and venipuncture, lidocaine and prilocaine cream should be applied under an occlusive dressing for at least 1 hour. To provide dermal analgesia for clinical procedures such as split skin graft harvesting, lidocaine and prilocaine cream should be applied under occlusive dressing for at least 2 hours. Satisfactory dermal analgesia is achieved 1 hour after application, reaches maximum at 2 to 3 hours, and persists for 1 to 2 hours after removal. Absorption from the genital mucosa is more rapid and onset time is shorter (5 to 10 minutes) than after application to intact skin. After a 5 to 10 minute application of lidocaine and prilocaine cream to female genital mucosa, the average duration of effective analgesia to an argon laser stimulus (which produced a sharp, pricking pain) was 15 to 20 minutes (individual variations in the range of 5 to 45 minutes).

Dermal application of lidocaine and prilocaine cream may cause a transient, local blanching followed by a transient, local redness or erythema.

Pharmacokinetics: Lidocaine and prilocaine cream is a eutectic mixture of lidocaine 2.5% and prilocaine 2.5% formulated as an oil in water emulsion. In this eutectic mixture, both anesthetics are liquid at room temperature (see DESCRIPTION) and the penetration and subsequent systemic absorption of both prilocaine and lidocaine are enhanced over that which would be seen if each component in crystalline form was applied separately as a 2.5% topical cream.

Absorption: The amount of lidocaine and prilocaine systemically absorbed from lidocaine and prilocaine cream is directly related to both the duration of application and to the area over which it is applied. In two pharmacokinetic studies, 60 g of lidocaine and prilocaine cream (1.5 g lidocaine and 1.5 g prilocaine) was applied to 400 cm2 of intact skin on the lateral thigh and then covered by an occlusive dressing. The subjects were then randomized such that one-half of the subjects had the occlusive dressing and residual cream removed after 3 hours, while the remainder left the dressing in place for 24 hours. The results from these studies are summarized below.

TABLE 1 Absorption of Lidocaine and Prilocaine from Lidocaine and Prilocaine Cream: Normal Volunteers (N=16)
*Maximum recommended duration of exposure is 4 hours.
Lidocaine and Prilocaine Cream (g) | Area (cm2) | Time on (hrs) | Drug Content (mg) | Absorbed (mg) | Cmax (µg/mL) | Tmax (hr)
60 | 400 | 3 | lidocaine 1500 | 54 | 0.12 | 4
 |  |  | prilocaine 1500 | 92 | 0.07 | 4
60 | 400 | 24* | lidocaine 1500 | 243 | 0.28 | 10
 |  |  | prilocaine 1500 | 503 | 0.14 | 10

When 60 g of lidocaine and prilocaine cream was applied over 400 cm2 for 24 hours, peak blood levels of lidocaine are approximately 1/20 the systemic toxic level. Likewise, the maximum prilocaine level is about 1/36 the toxic level. In a pharmacokinetic study, lidocaine and prilocaine cream was applied to penile skin in 20 adult male patients in doses ranging from 0.5 g to 3.3 g for 15 minutes. Plasma concentrations of lidocaine and prilocaine following lidocaine and prilocaine cream application in this study were consistently low (2.5 to 16 ng/mL for lidocaine and 2.5 to 7 ng/mL for prilocaine). The application of lidocaine and prilocaine cream to broken or inflamed skin, or to 2,000 cm2 or more of skin where more of both anesthetics are absorbed, could result in higher plasma levels that could, in susceptible individuals, produce a systemic pharmacologic response.

The absorption of lidocaine and prilocaine cream applied to genital mucous membranes was studied in two open-label clinical trials. Twenty-nine patients received 10 g of lidocaine and prilocaine cream applied for 10 to 60 minutes in the vaginal fornices. Plasma concentrations of lidocaine and prilocaine following lidocaine and prilocaine cream application in these studies ranged from 148 to 641 ng/mL for lidocaine and 40 to 346 ng/mL for prilocaine and time to reach maximum concentration (tmax) ranged from 21 to 125 minutes for lidocaine and from 21 to 95 minutes for prilocaine. These levels are well below the concentrations anticipated to give rise to systemic toxicity (approximately 5000 ng/mL for lidocaine and prilocaine).

Distribution: When each drug is administered intravenously, the steady-state volume of distribution is 1.1 to 2.1 L/kg (mean 1.5, ±0.3 SD, n=13) for lidocaine and is 0.7 to 4.4 L/kg (mean 2.6, ±1.3 SD, n=13) for prilocaine. The larger distribution volume for prilocaine produces the lower plasma concentrations of prilocaine observed when equal amounts of prilocaine and lidocaine are administered. At concentrations produced by application of lidocaine and prilocaine cream, lidocaine is approximately 70% bound to plasma proteins, primarily alpha-1-acid glycoprotein. At much higher plasma concentrations (1 to 4 µg/mL of free base) the plasma protein binding of lidocaine is concentration dependent. Prilocaine is 55% bound to plasma proteins. Both lidocaine and prilocaine cross the placental and blood brain barrier, presumably by passive diffusion.

Metabolism: It is not known if lidocaine or prilocaine are metabolized in the skin. Lidocaine is metabolized rapidly by the liver to a number of metabolites including monoethylglycinexylidide (MEGX) and glycinexylidide (GX), both of which have pharmacologic activity similar to, but less potent than that of lidocaine. The metabolite, 2,6-xylidine, has unknown pharmacologic activity. Following intravenous administration, MEGX and GX concentrations in serum range from 11 to 36% and from 5 to 11% of lidocaine concentrations, respectively. Prilocaine is metabolized in both the liver and kidneys by amidases to various metabolites including ortho -toluidine and N-n-propylalanine. It is not metabolized by plasma esterases. The ortho -toluidine metabolite has been shown to be carcinogenic in several animal models (see PRECAUTIONS, Carcinogenesis). In addition, ortho -toluidine can produce methemoglobinemia following systemic doses of prilocaine approximating 8 mg/kg (see ADVERSE REACTIONS). Very young patients, patients with glucose-6-phosphate dehydro- genase deficiencies and patients taking oxidizing drugs such as antimalarials and sulfonamides are more susceptible to methemoglobinemia (see WARNINGS, Methemoglobinemia).

Elimination: The terminal elimination half-life of lidocaine from the plasma following IV administration is approximately 65 to 150 minutes (mean 110, ±24 SD, n=13). More than 98% of an absorbed dose of lidocaine can be recovered in the urine as metabolites or parent drug. The systemic clearance is 10 to 20 mL/min/kg (mean 13, ±3 SD, n=13). The elimination half-life of prilocaine is approximately 10 to 150 minutes (mean 70, ±48 SD, n=13). The systemic clearance is 18 to 64 mL/min/kg (mean 38, ±15 SD, n=13). During intravenous studies, the elimination half-life of lidocaine was statistically significantly longer in elderly patients (2.5 hours) than in younger patients (1.5 hours). No studies are available on the intravenous pharmacokinetics of prilocaine in elderly patients.

Pediatrics: Some pharmacokinetic (PK) data are available in infants (1 month to <2 years old) and children (2 to <12 years old). One PK study was conducted in 9 full-term neonates (mean age: 7 days and mean gestational age: 38.8 weeks). The study results show that neonates had comparable plasma lidocaine and prilocaine concentrations and blood methemoglobin concentrations as those found in previous pediatric PK studies and clinical trials. There was a tendency towards an increase in methemoglobin formation. However, due to assay limitations and very little amount of blood that could be collected from neonates, large variations in the above reported concentrations were found.

Special Populations: No specific PK studies were conducted. The half-life may be increased in cardiac or hepatic dysfunction. Prilocaine's half-life also may be increased in hepatic or renal dysfunction since both of these organs are involved in prilocaine metabolism.

CLINICAL STUDIES

Lidocaine and prilocaine cream application in adults prior to IV cannulation or venipuncture was studied in 200 patients in four clinical studies in Europe. Application for at least 1 hour provided significantly more dermal analgesia than placebo cream or ethyl chloride. Lidocaine and prilocaine cream was comparable to subcutaneous lidocaine, but was less efficacious than intradermal lidocaine. Most patients found lidocaine and prilocaine cream treatment preferable to lidocaine infiltration or ethyl chloride spray.

Lidocaine and prilocaine cream was compared with 0.5% lidocaine infiltration prior to skin graft harvesting in one open label study in 80 adult patients in England. Application of lidocaine and prilocaine cream for 2 to 5 hours provided dermal analgesia comparable to lidocaine infiltration.

Lidocaine and prilocaine cream application in children was studied in seven non-US studies (320 patients) and one US study (100 patients). In controlled studies, application of lidocaine and prilocaine cream for at least 1 hour with or without presurgical medication prior to needle insertion provided significantly more pain reduction than placebo. In children under the age of seven years, lidocaine and prilocaine cream was less effective than in older children or adults.

Lidocaine and prilocaine cream was compared with placebo in the laser treatment of facial port-wine stains in 72 pediatric patients (ages 5 to 16). Lidocaine and prilocaine cream was effective in providing pain relief during laser treatment.

Lidocaine and prilocaine cream alone was compared with lidocaine and prilocaine cream followed by lidocaine infiltration and lidocaine infiltration alone prior to cryotherapy for the removal of male genital warts. The data from 121 patients demonstrated that lidocaine and prilocaine cream was not effective as a sole anesthetic agent in managing the pain from the surgical procedure. The administration of lidocaine and prilocaine cream prior to lidocaine infiltration provided significant relief of discomfort associated with local anesthetic infiltration and thus was effective in the overall reduction of pain from the procedure only when used in conjunction with local anesthetic infiltration of lidocaine.

Lidocaine and prilocaine cream was studied in 105 full term neonates (gestational age: 37 weeks) for blood drawing and circumcision procedures. When considering the use of lidocaine and prilocaine cream in neonates, the primary concerns are the systemic absorption of the active ingredients and the subsequent formation of methemoglobin. In clinical studies performed in neonates, the plasma levels of lidocaine, prilocaine, and methemoglobin were not reported in a range expected to cause clinical symptoms.

Local dermal effects associated with lidocaine and prilocaine cream application in these studies on intact skin included paleness, redness and edema and were transient in nature (see ADVERSE REACTIONS).

The application of lidocaine and prilocaine cream on genital mucous membranes for minor, superficial surgical procedures (eg, removal of condylomata acuminata) was studied in 80 patients in a placebo-controlled clinical trial (60 patients received lidocaine and prilocaine cream and 20 patients received placebo). Lidocaine and prilocaine cream (5 to 10 g) applied between 1 and 75 minutes before surgery, with a median time of 15 minutes, provided effective local anesthesia for minor superficial surgical procedures. The greatest extent of analgesia, as measured by VAS scores, was attained after 5 to 15 minutes' application. The application of lidocaine and prilocaine cream to genital mucous membranes as pretreatment for local anesthetic infiltration was studied in a double-blind, placebo-controlled study in 44 female patients (21 patients received lidocaine and prilocaine cream and 23 patients received placebo) scheduled for infiltration prior to a surgical procedure of the external vulva or genital mucosa. Lidocaine and prilocaine cream applied to the genital mucous membranes for 5 to 10 minutes resulted in adequate topical anesthesia for local anesthetic injection.

Individualization of Dose: The dose of lidocaine and prilocaine cream that provides effective analgesia depends on the duration of the application over the treated area.

All pharmacokinetic and clinical studies employed a thick layer of lidocaine and prilocaine cream (1 to 2 g/10 cm2). The duration of application prior to venipuncture was 1 hour. The duration of application prior to taking split thickness skin grafts was 2 hours. A thinner application has not been studied and may result in less complete analgesia or a shorter duration of adequate analgesia.

The systemic absorption of lidocaine and prilocaine is a side effect of the desired local effect. The amount of drug absorbed depends on surface area and duration of application. The systemic blood levels depend on the amount absorbed and patient size (weight) and the rate of systemic drug elimination. Long duration of application, large treatment area, small patients, or impaired elimination may result in high blood levels. The systemic blood levels are typically a small fraction (1/20 to 1/36) of the blood levels that produce toxicity. Table 2 below gives maximum recommended doses, application areas and application times for infants and children.

TABLE 2 LIDOCAINE AND PRILOCAINE CREAM MAXIMUM RECOMMENDED DOSE, APPLICATION AREA, AND APPLICATION TIME BY AGE AND WEIGHT* For Infants and Children Based on Application to Intact Skin
Please note: If a patient greater than 3 months old does not meet the minimum weight requirement, the maximum total dose of lidocaine and prilocaine cream should be restricted to that which corresponds to the patient's weight.
* These are broad guidelines for avoiding systemic toxicity in applying lidocaine and prilocaine cream to patients with normal intact skin and with normal renal and hepatic function.
** For more individualized calculation of how much lidocaine and prilocaine may be absorbed, physicians can use the following estimates of lidocaine and prilocaine absorption for children and adults:
The estimated mean (±SD) absorption of lidocaine is 0.045 (±0.016) mg/cm2/hr.
The estimated mean (±SD) absorption of prilocaine is 0.077 (±0.036) mg/cm2/hr.
Age and Body Weight Requirements | Maximum Total Dose of Lidocaine and Prilocaine cream | Maximum Application Area** | Maximum Application Time
0 up to 3 months or < 5 kg | 1 g | 10 cm2 | 1 hour
3 up to 12 months and > 5 kg | 2 g | 20 cm2 | 4 hours
1 to 6 years and > 10 kg | 10 g | 100 cm2 | 4 hours
7 to 12 years and > 20 kg | 20 g | 200 cm2 | 4 hours

An I.V. antiarrhythmic dose of lidocaine is 1 mg/kg (70 mg/70 kg) and gives a blood level of about 1 µg/mL. Toxicity would be expected at blood levels above 5 µg/mL. Smaller areas of treatment are recommended in a debilitated patient, a small child or a patient with impaired elimination. Decreasing the duration of application is likely to decrease the analgesic effect.

INDICATIONS AND USAGE

Lidocaine and prilocaine cream (a eutectic mixture of lidocaine 2.5% and prilocaine 2.5%) is indicated as a topical anesthetic for use on:

- normal intact skin for local analgesia.

- genital mucous membranes for superficial minor surgery and as pretreatment for infiltration anesthesia.

Lidocaine and prilocaine cream is not recommended in any clinical situation when penetration or migration beyond the tympanic membrane into the middle ear is possible because of the ototoxic effects observed in animal studies (see WARNINGS).

CONTRAINDICATIONS

Lidocaine and prilocaine cream (lidocaine 2.5% and prilocaine 2.5%) is contraindicated in patients with a known history of sensitivity to local anesthetics of the amide type or to any other component of the product.

WARNINGS

Application of lidocaine and prilocaine cream to larger areas or for longer times than those recommended could result in sufficient absorption of lidocaine and prilocaine resulting in serious adverse effects (see Individualization of Dose).

Patients treated with class III anti-arrhythmic drugs (e.g., amiodarone, bretylium, sotalol, dofetilide) should be under close surveillance and ECG monitoring considered, because cardiac effects may be additive.

Studies in laboratory animals (guinea pigs) have shown that lidocaine and prilocaine cream has an ototoxic effect when instilled into the middle ear. In these same studies, animals exposed to lidocaine and prilocaine cream only in the external auditory canal, showed no abnormality. Lidocaine and prilocaine cream should not be used in any clinical situation when its penetration or migration beyond the tympanic membrane into the middle ear is possible.

Methemoglobinemia: Lidocaine and prilocaine cream should not be used in those rare patients with congenital or idiopathic methemoglobinemia and in infants under the age of twelve months who are receiving treatment with methemoglobin-inducing agents.

Very young patients or patients with glucose-6-phosphate dehydrogenase deficiencies are more susceptible to methemoglobinemia.

Patients taking drugs associated with drug-induced methemoglobinemia such as sulfonamides, acetaminophen, acetanilid, aniline dyes, benzocaine, chloroquine, dapsone, naphthalene, nitrates and nitrites, nitrofurantoin, nitroglycerin, nitroprusside, pamaquine, para-aminosalicylic acid, phenacetin, phenobarbital, phenytoin, primaquine, quinine, are also at greater risk for developing methemoglobinemia.

There have been reports of significant methemoglobinemia (20 to 30%) in infants and children following excessive applications of lidocaine and prilocaine cream. These cases involved the use of large doses, larger than recommended areas of application, or infants under the age of 3 months who did not have fully mature enzyme systems. In addition, a few of these cases involved the concomitant administration of methemoglobin-inducing agents. Most patients recovered spontaneously after removal of the cream. Treatment with IV methylene blue may be effective if required.

Physicians are cautioned to make sure that parents orother caregivers understand the need for careful application of lidocaine and prilocaine cream, to ensure that the doses and areas of application recommended in Table 2 are not exceeded (especially in children under the age of 3 months) and to limit the period of application to the minimum required to achieve the desired anesthesia.

Neonates and infants up to 3 months of age should be monitored for Met-Hb levels before, during, and after the application of lidocaine and prilocaine cream, provided the test results can be obtained quickly.

PRECAUTIONS

General: Repeated doses of lidocaine and prilocaine cream may increase blood levels of lidocaine and prilocaine. Lidocaine and prilocaine cream should be used with caution in patients who may be more sensitive to the systemic effects of lidocaine and prilocaine including acutely ill, debilitated, or elderly patients.

Lidocaine and prilocaine cream should not be applied to open wounds.

Care should be taken not to allow lidocaine and prilocaine cream to come in contact with the eye because animal studies have demonstrated severe eye irritation. Also the loss of protective reflexes can permit corneal irritation and potential abrasion. Absorption of lidocaine and prilocaine cream in conjunctival tissues has not been determined. If eye contact occurs, immediately wash out the eye with water or saline and protect the eye until sensation returns.

Patients allergic to paraaminobenzoic acid derivatives (procaine, tetracaine, benzocaine, etc.) have not shown cross sensitivity to lidocaine and/or prilocaine, however, lidocaine and prilocaine cream should be used with caution in patients with a history of drug sensitivities, especially if the etiologic agent is uncertain.

Patients with severe hepatic disease, because of their inability to metabolize local anesthetics normally, are at greater risk of developing toxic plasma concentrations of lidocaine and prilocaine.

Lidocaine and prilocaine have been shown to inhibit viral and bacterial growth. The effect of lidocaine and prilocaine cream on intradermal injections of live vaccines has not been determined.

Information for Patients: When lidocaine and prilocaine cream is used, the patient should be aware that the production of dermal analgesia may be accompanied by the block of all sensations in the treated skin. For this reason, the patient should avoid inadvertent trauma to the treated area by scratching, rubbing, or exposure to extreme hot or cold temperatures until complete sensation has returned.

Lidocaine and prilocaine cream should not be applied near the eyes or on open wounds.

Drug Interactions: Lidocaine and prilocaine cream should be used with caution in patients receiving Class I antiarrhythmic drugs (such as tocainide and mexiletine) since the toxic effects are additive and potentially synergistic.

Prilocaine may contribute to the formation of methemoglobin in patients treated with other drugs known to cause this condition (see WARNINGS, Methemoglobinemia).

Specific interaction studies with lidocaine/prilocaine and class III anti-arrhythmic drugs (e.g., amiodarone, bretylium, sotalol, doetilide) have not been performed, but caution is advised (see WARNINGS).

Should lidocaine and prilocaine cream be used concomitantly with other products containing lidocaine and/or prilocaine, cumulative doses from all formulations must be considered.

Carcinogenesis, Mutagenesis, Impairment of Fertility

Carcinogenesis: Long-term studies in animals designed to evaluate the carcinogenic potential of lidocaine and prilocaine have not been conducted.

Metabolites of prilocaine have been shown to be carcinogenic in laboratory animals. In the animal studies reported below, doses or blood levels are compared with the Single Dermal Administration (SDA) of 60 g of lidocaine and prilocaine cream to 400 cm2 for 3 hours to a small person (50 kg). The typical application of lidocaine and prilocaine cream for one or two treatments for venipuncture sites (2.5 or 5 g) would be 1/24 or 1/12 of that dose in an adult or about the same mg/kg dose in an infant.

Chronic oral toxicity studies of ortho -toluidine, a metabolite of prilocaine, in mice (450 to 7200 mg/m2; 60 to 960 times SDA) and rats (900 to 4,800 mg/m2; 60 to 320 times SDA) have shown that ortho -toluidine is a carcinogen in both species. The tumors included hepatocarcinomas/adenomas in female mice, multiple occurrences of hemangiosarcomas/hemangiomas in both sexes of mice, sarcomas of multiple organs, transitional-cell carcinomas/papillomas of urinary bladder in both sexes of rats, subcutaneous fibromas/fibrosarcomas and mesotheliomas in male rats, and mammary gland fibroadenomas/adenomas in female rats. The lowest dose tested (450 mg/m2 in mice, 900 mg/m2 in rats; 60 times SDA) was carcinogenic in both species. Thus the no-effect dose must be less than 60 times SDA. The animal studies were conducted at 150 to 2,400 mg/kg in mice and at 150 to 800 mg/kg in rats. The dosages have been converted to mg/m2 for the SDA calculations above.

Mutagenesis: The mutagenic potential of lidocaine HCl has been tested in a bacterial reverse (Ames) assay in Salmonella, an in vitro chromosomal aberration assay using human lymphocytes an in vivo micronucleus test in mice. There was no indication of mutagenicity or structural damage to chromosomes in these tests.

Ortho -toluidine, a metabolite of prilocaine, at a concentration of 0.5 µg/mL, was genotoxic in Escherichia coli DNA repair and phage-induction assays. Urine concentrates from rats treated with ortho -toluidine (300 mg/kg orally; 300 times SDA) were mutagenic when examined in Salmonella typhimurium in the presence of metabolic activation. Several other tests on ortho -toluidine, including reverse mutations in five different Salmonella typhimurium strains in the presence or absence of metabolic activation and a study to detect single strand breaks in DNA of V79 Chinese hamster cells, were negative.

Impairment of Fertility: See Use in Pregnancy .

Use in Pregnancy: Teratogenic Effects: Pregnancy Category B.

Reproduction studies with lidocaine have been performed in rats and have revealed no evidence of harm to the fetus (30 mg/kg subcutaneously; 22 times SDA). Reproduction studies with prilocaine have been performed in rats and have revealed no evidence of impaired fertility or harm to the fetus (300 mg/kg intramuscularly; 188 times SDA). There are, however, no adequate and well-controlled studies in pregnant women. Because animal reproduction studies are not always predictive of human response, lidocaine and prilocaine cream should be used during pregnancy only if clearly needed.

Reproduction studies have been performed in rats receiving subcutaneous administration of an aqueous mixture containing lidocaine HCl and prilocaine HCl at 1:1 (w/w). At 40 mg/kg each, a dose equivalent to 29 times SDA lidocaine and 25 times SDA prilocaine, no teratogenic, embryotoxic or fetotoxic effects were observed.

Labor and Delivery : Neither lidocaine nor prilocaine are contraindicated in labor and delivery. Should lidocaine and prilocaine cream be used concomitantly with other products containing lidocaine and/or prilocaine, cumulative doses from all formulations must be considered.

Nursing Mothers: Lidocaine, and probably prilocaine, are excreted in human milk. Therefore, caution should be exercised when lidocaine and prilocaine cream is administered to a nursing mother since the milk:plasma ratio of lidocaine is 0.4 and is not determined for prilocaine.

Pediatric Use: Controlled studies of lidocaine and prilocaine cream in children under the age of seven years have shown less overall benefit than in older children or adults. These results illustrate the importance of emotional and psychological support of younger children undergoing medical or surgical procedures.

Lidocaine and prilocaine cream should be used with care in patients with conditions or therapy associated with methemoglobinemia (see WARNINGS, Methemoglobinemia).

When using lidocaine and prilocaine cream in young children, especially infants under the age of 3 months, care must be taken to insure that the caregiver understands the need to limit the dose and area of application, and to prevent accidental ingestion (see DOSAGE AND ADMINISTRATION and WARNINGS,Methemoglobinemia).

In neonates (minimum gestation age: 37 weeks) and children weighing less than 20 kg, the area and duration of application should be limited (see TABLE 2 in Individualization of Dose).

Studies have not demonstrated the efficacy of lidocaine and prilocaine cream for heel lancing in neonates.

Geriatric Use: Of the total number of patients in clinical studies of lidocaine and prilocaine cream, 180 were age 65 to 74 and 138 were 75 and over. No overall differences in safety or efficacy were observed between these patients and younger patients. Other reported clinical experience has not identified differences in responses between the elderly and younger patients, but greater sensitivity of some older individuals cannot be ruled out.

Plasma levels of lidocaine and prilocaine in geriatric and non-geriatric patients following application of a thick layer of lidocaine and prilocaine cream are very low and well below potentially toxic levels. However, there are no sufficient data to evaluate quantitative differences in systemic plasma levels of lidocaine and prilocaine between geriatric and non-geriatric patients following application of lidocaine and prilocaine cream.

Consideration should be given for those elderly patients who have enhanced sensitivity to systemic absorption (see PRECAUTIONS).

After intravenous dosing, the elimination half-life of lidocaine is significantly longer in elderly patients (2.5 hours) than in younger patients (1.5 hours). (See CLINICAL PHARMACOLOGY).

ADVERSE REACTIONS

Localized Reactions: During or immediately after treatment with lidocaine and prilocaine cream on intact skin, the skin at the site of treatment may develop erythema or edema or may be the locus of abnormal sensation. Rare cases of discrete purpuric or petechial reactions at the application site have been reported. Rare cases of hyperpigmentation following the use of lidocaine and prilocaine cream have been reported. The relationship to lidocaine and prilocaine cream or the underlying procedure has not been established. In clinical studies on intact skin involving over 1,300 lidocaine and prilocaine cream-treated subjects, one or more such local reactions were noted in 56% of patients, and were generally mild and transient, resolving spontaneously within 1 or 2 hours. There were no serious reactions that were ascribed to lidocaine and prilocaine cream.

Two recent reports describe blistering on the foreskin in neonates about to undergo circumcision. Both neonates received 1.0 g of lidocaine and prilocaine cream.

In patients treated with lidocaine and prilocaine cream on intact skin, local effects observed in the trials included: paleness (pallor or blanching) 37%, redness (erythema) 30%, alterations in temperature sensations 7%, edema 6%, itching 2% and rash, less than 1%.

In clinical studies on genital mucous membranes involving 378 lidocaine and prilocaine cream-treated patients, one or more application site reactions, usually mild and transient, were noted in 41% of patients. The most common application site reactions were redness (21%), burning sensation (17%) and edema (10%).

Allergic Reactions: Allergic and anaphylactoid reactions associated with lidocaine or prilocaine can occur. They are characterized by urticaria, angioedema, bronchospasm, and shock. If they occur they should be managed by conventional means. The detection of sensitivity by skin testing is of doubtful value.

Systemic (Dose Related) Reactions: Systemic adverse reactions following appropriate use of lidocaine and prilocaine cream are unlikely due to the small dose absorbed (see CLINICAL PHARMACOLOGY, Pharmacokinetics). Systemic adverse effects of lidocaine and/or prilocaine are similar in nature to those observed with other amide local anesthetic agents including CNS excitation and/or depression (light-headedness, nervousness, apprehension, euphoria, confusion, dizziness, drowsiness, tinnitus, blurred or double vision, vomiting, sensations of heat, cold or numbness, twitching, tremors, convulsions, unconsciousness, respiratory depression and arrest). Excitatory CNS reactions may be brief or not occur at all, in which case the first manifestation may be drowsiness merging into unconsciousness. Cardiovascular manifestations may include bradycardia, hypotension and cardiovascular collapse leading to arrest.

OVERDOSAGE

Peak blood levels following a 60 g application to 400 cm2 of intact skin for 3 hours are 0.05 to 0.16 µg/mL for lidocaine and 0.02 to 0.10 µg/mL for prilocaine. Toxic levels of lidocaine (>5 µg/mL) and/or prilocaine (>6 µg/mL) cause decreases in cardiac output, total peripheral resistance and mean arterial pressure. These changes may be attributable to direct depressant effects of these local anesthetic agents on the cardiovascular system. In the absence of massive topical overdose or oral ingestion, evaluation should include evaluation of other etiologies for the clinical effects or overdosage from other sources of lidocaine, prilocaine or other local anesthetics. Consult the package inserts for parenteral Xylocaine (lidocaine HCl) or Citanest (prilocaine HCl) for further information for the management of overdose.

DOSAGE AND ADMINISTRATION

Adult Patients-Intact Skin

A thick layer of lidocaine and prilocaine cream is applied to intact skin and covered with an occlusive dressing (see INSTRUCTIONS FOR APPLICATION).

Minor Dermal Procedures: For minor procedures such as intravenous cannulation and venipuncture, apply 2.5 grams of lidocaine and prilocaine cream (1/2 the 5 g tube) over 20 to 25 cm2 of skin surface for at least 1 hour. In controlled clinical trials using lidocaine and prilocaine cream, two sites were usually prepared in case there was a technical problem with cannulation or venipuncture at the first site.

Major Dermal Procedures: For more painful dermatological procedures involving a larger skin area such as split thickness skin graft harvesting, apply 2 grams of lidocaine and prilocaine cream per 10 cm2 of skin and allow to remain in contact with the skin for at least 2 hours.

Adult Male Genital Skin: As an adjunct prior to local anesthetic infiltration, apply a thick layer of lidocaine and prilocaine cream (1 g/10 cm2) to the skin surface for 15 minutes. Local anesthetic infiltration should be performed immediately after removal of lidocaine and prilocaine cream.

Dermal analgesia can be expected to increase for up to 3 hours under occlusive dressing and persist for 1 to 2 hours after removal of the cream. The amount of lidocaine and prilocaine absorbed during the period of application can be estimated from the information in Table 2, ** footnote, in Individualization of Dose .

Adult Female Patients-Genital Mucous Membranes

For minor procedures on the female external genitalia, such as removal of condylomata acuminata, as well as for use as pretreatment for anesthetic infiltration, apply a thick layer (5 to 10 grams) of lidocaine and prilocaine cream for 5 to 10 minutes.

Occlusion is not necessary for absorption, but may be helpful to keep the cream in place. Patients should be lying down during the lidocaine and prilocaine cream application, especially if no occlusion is used. The procedure or the local anesthetic infiltration should be performed immediately after the removal of lidocaine and prilocaine cream.

Pediatric Patients-Intact Skin

The following are the maximum recommended doses, application areas and application times for lidocaine and prilocaine cream based on a child's age and weight:

Age and Body Weight Requirements | Maximum Total Dose of Lidocaine and Prilocaine Cream | Maximum Application Area | Maximum Application Time
0 up to 3 months or < 5 kg | 1 g | 10 cm2 | 1 hour
3 up to 12 months and > 5 kg | 2 g | 20 cm2 | 4 hours
1 to 6 years and > 10 kg | 10 g | 100 cm2 | 4 hours
7 to 12 years and > 20 kg | 20 g | 200 cm2 | 4 hours

Please note: If a patient greater than 3 months old does not meet the minimum weight requirement, the maximum total dose of lidocaine and prilocaine cream should be restricted to that which corresponds to the patient's weight (see INSTRUCTIONS FOR APPLICATION).

Practitioners should carefully instruct caregivers to avoid application of excessive amounts of lidocaine and prilocaine cream (see PRECAUTIONS).

When applying lidocaine and prilocaine cream to the skin of young children, care must be taken to maintain careful observation of the child to prevent accidental ingestion of lidocaine and prilocaine cream or the occlusive dressing. A secondary protective covering to prevent inadvertent disruption of the application site may be useful.

Lidocaine and prilocaine cream should not be used in neonates with a gestational age less than 37 weeks nor in infants under the age of 12 months who are receiving treatment with methemoglobin-inducing agents (see WARNINGS, Methemoglobinemia).

When lidocaine and prilocaine cream (lidocaine 2.5% and prilocaine 2.5%) is used concomitantly with other products containing local anesthetic agents, the amount absorbed from all formulations must be considered (see Individualization of Dose). The amount absorbed in the case of lidocaine and prilocaine cream is determined by the area over which it is applied and the duration of application under occlusion (see Table 2, ** footnote, in Individualization of Dose).

Although the incidence of systemic adverse reactions with lidocaine and prilocaine cream is very low, caution should be exercised, particularly when applying it over large areas and leaving it on for longer than 2 hours. The incidence of systemic adverse reactions can be expected to be directly proportional to the area and time of exposure (see Individualization of Dose).

INSTRUCTIONS FOR APPLICATION:

To measure 1 gram of lidocaine and prilocaine cream, the Cream should be gently squeezed out of the tube as a narrow strip that is 1.5 inches (3.8 cm) long and 0.2 inches (5 mm) wide. The strip of lidocaine and prilocaine cream should be contained within the lines of the diagram shown below.

Use the number of strips that equals your dose, like the examples in the table below.

Dosing Information

1 gram = 1 strip
2 grams = 2 strips
2.5 grams = 2.5 strips

For adult and pediatric patients, apply ONLY as prescribed by your physician.

If your child is below the age of 3 months or small for their age, please inform your doctor before applying lidocaine and prilocaine cream, which can be harmful, if applied over too much skin at one time in young children.

When applying lidocaine and prilocaine cream to the intact skin of young children, it is important that they be carefully observed by an adult in order to prevent the accidental ingestion of or eye contact with lidocaine and prilocaine cream.

Lidocaine and prilocaine cream must be applied to intact skin at least 1 hour before the start of a routine procedure and for 2 hours before the start of a painful procedure. A protective covering of the cream is not necessary for absorption but may be helpful to keep the cream in place.

If using a protective covering, your doctor will remove it, wipe off the lidocaine and prilocaine cream, and clean the entire area with an antiseptic solution before the procedure. The duration of effective skin anesthesia will be at least 1 hour after removal of the protective covering.

Precautions

1. Do not apply near eyes or open wounds.
2. Keep out of the reach of children.
3. If your child becomes very dizzy, excessively sleepy, or develops duskiness of the face or lips after applying lidocaine and prilocaine cream, remove the cream and contact the child's physician at once.

HOW SUPPLIED

Lidocaine 2.5% and Prilocaine 2.5% Cream, USP is available as the following:

NDC No. | Strength | Size
NDC 0591-2070-26 | 5 gram/tube | packed individually.
NDC 0591-2070-72 | 5 gram/tube | packed in 5.
NDC 0591-2070-30 | 30 gram/tube | packed individually, in a child-resistant tube.

NOT FOR OPHTHALMIC USE.

KEEP CONTAINER TIGHTLY CLOSED AT ALL TIMES WHEN NOT IN USE.

Storage: Store at 20º to 25ºC (68º to 77ºF) [see USP Controlled Room Temperature].

Rx only

Keep out of the reach of children.

For all medical inquiries contact:
ACTAVIS
Medical Communications
Parsippany, NJ 07054
1-800-272-5525

Manufactured By:
IGI Laboratories Inc.
Buena, NJ 08310 USA

Distributed By:
Actavis Pharma, Inc.
Parsippany, NJ 07054 USA

Content Updated: June 2014
76626

PACKAGE LABEL.PRINCIPAL DISPLAY PANEL

Inflammation Reduction Pack